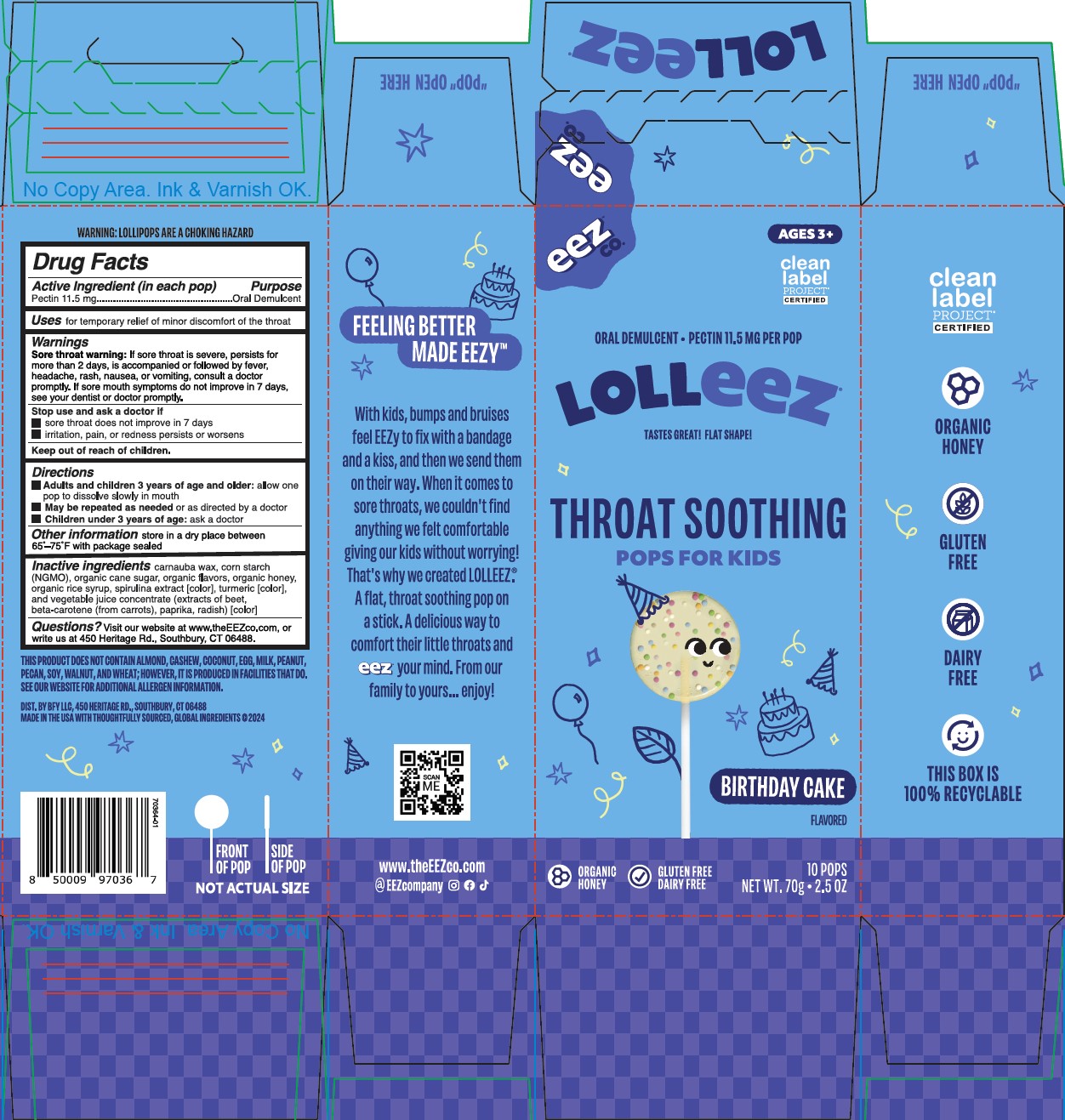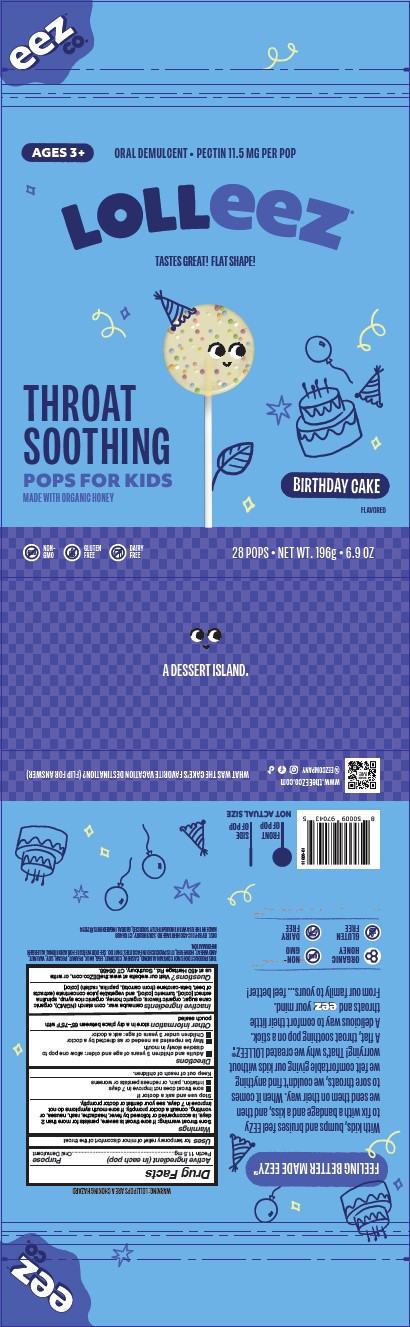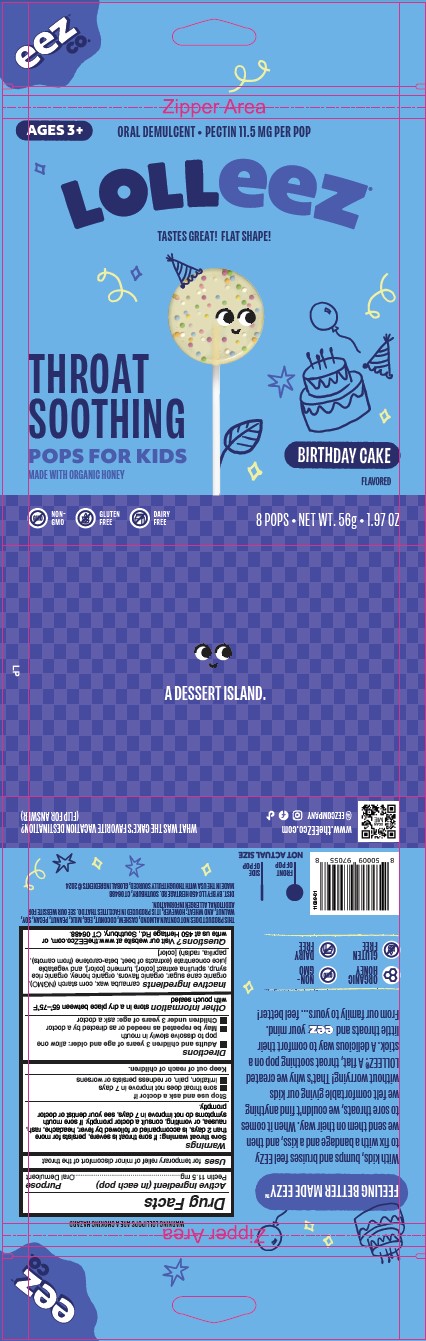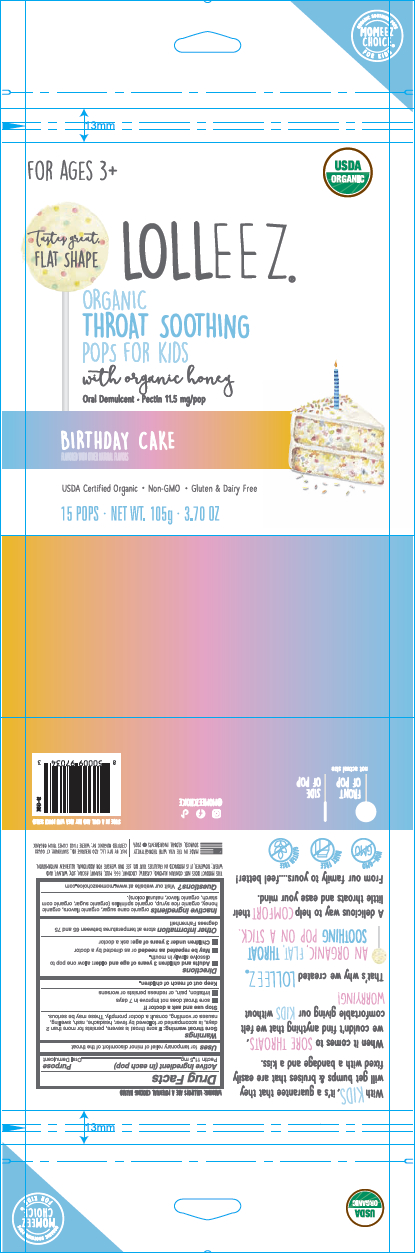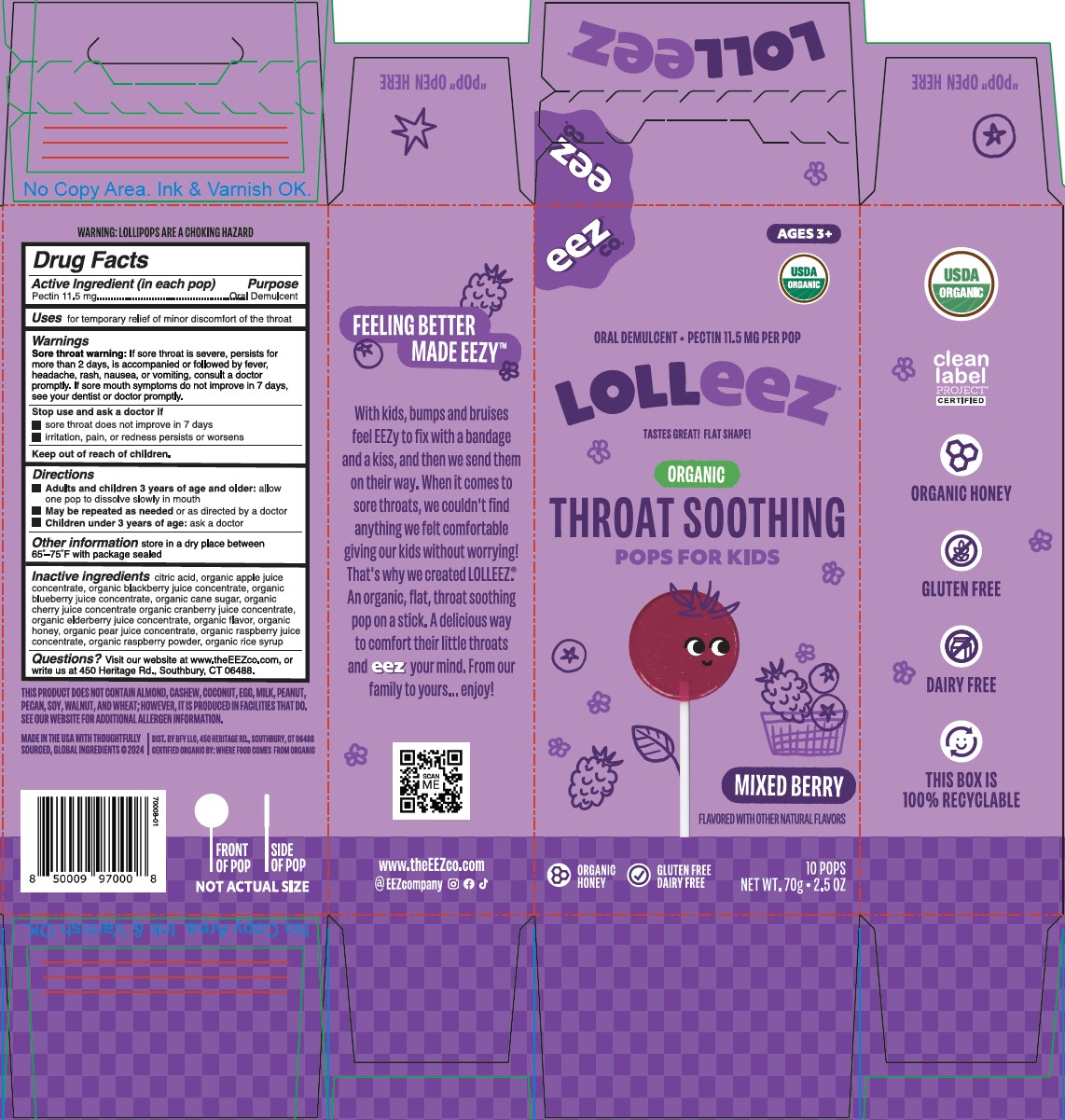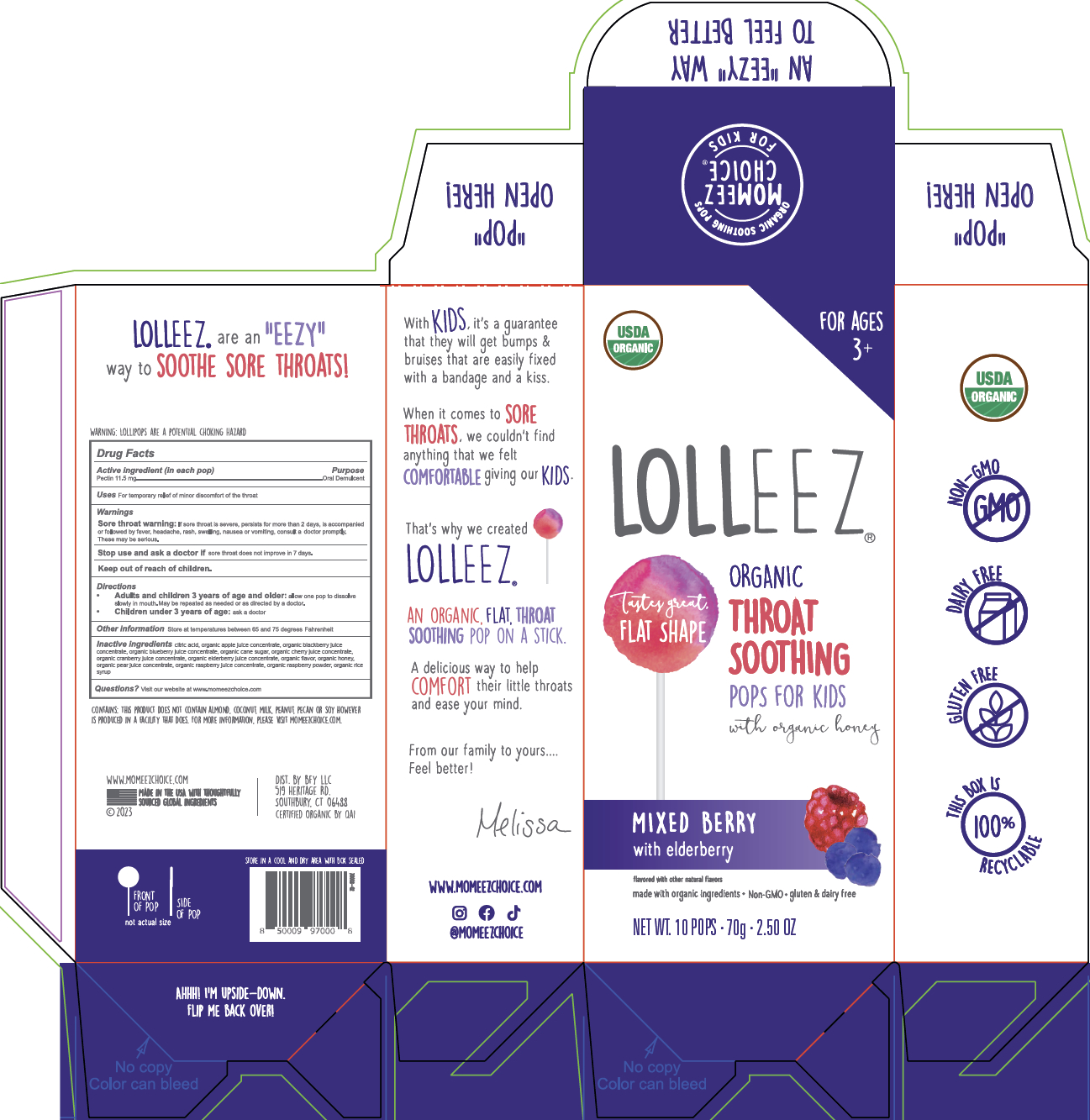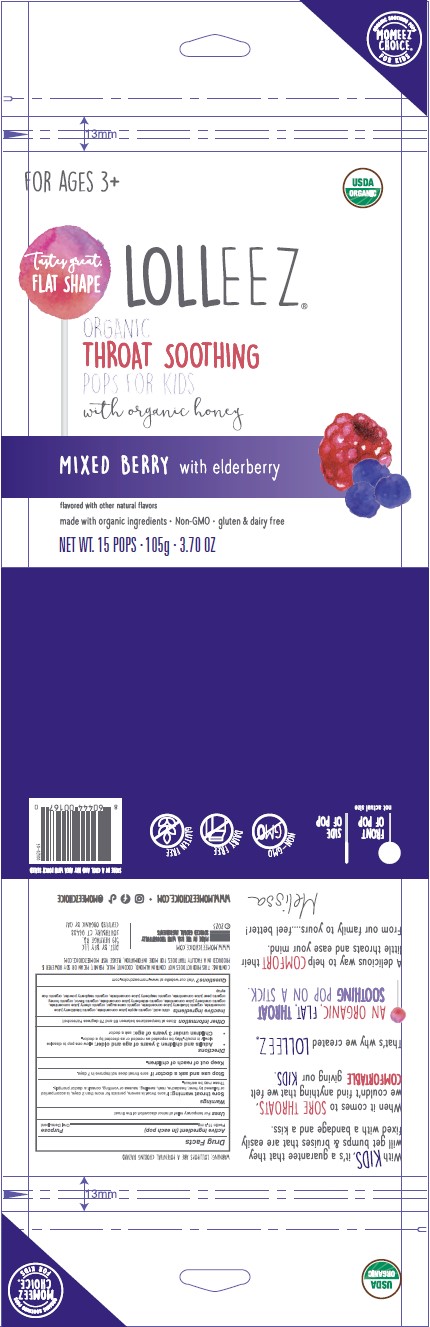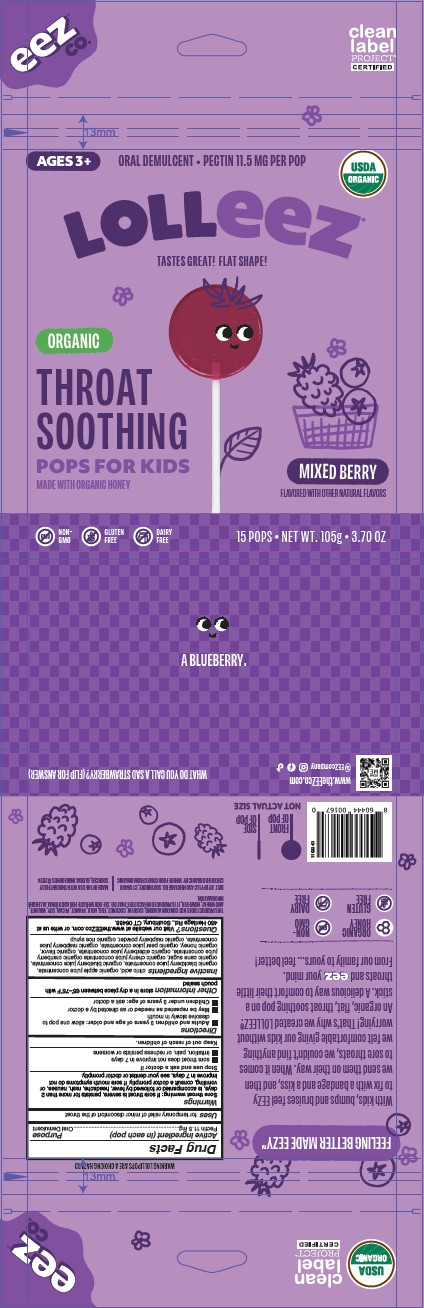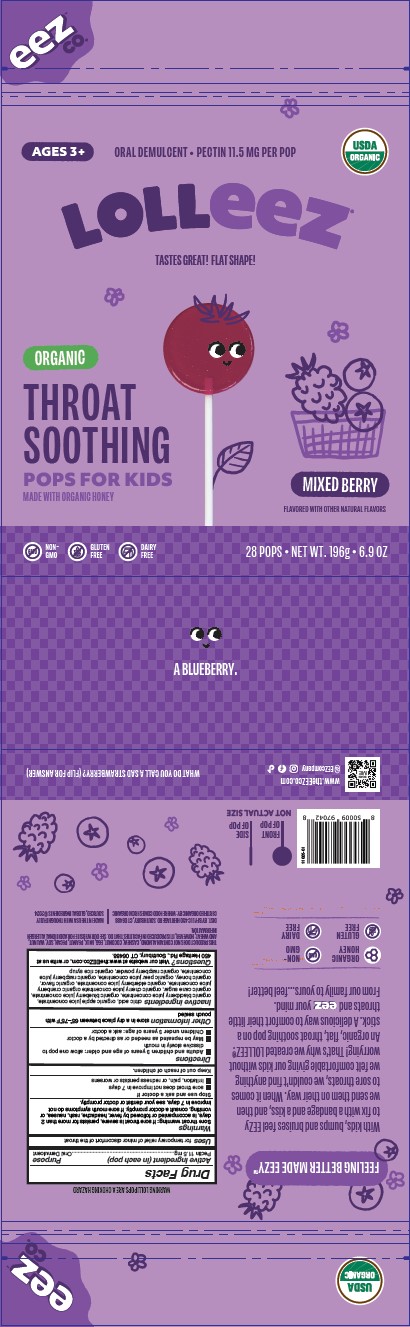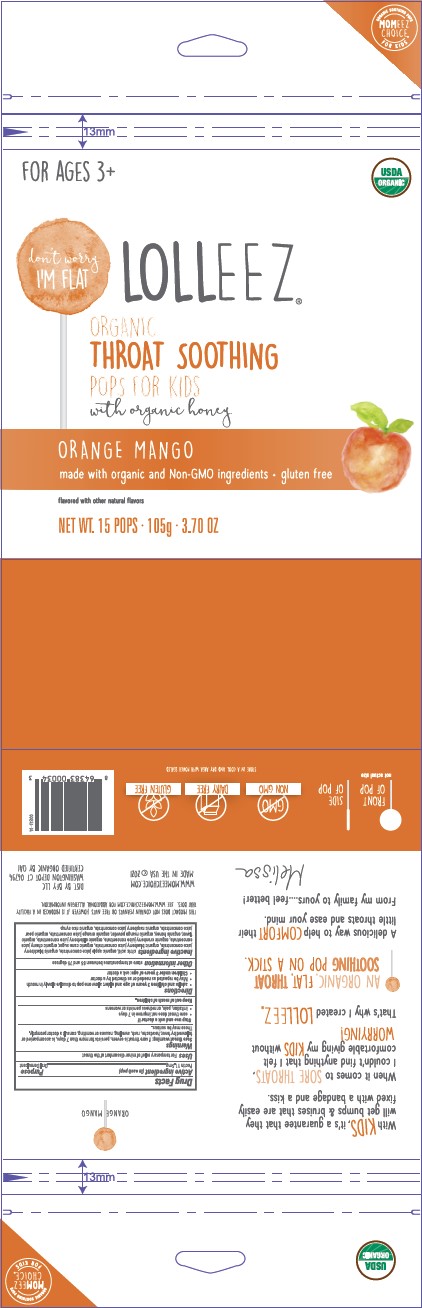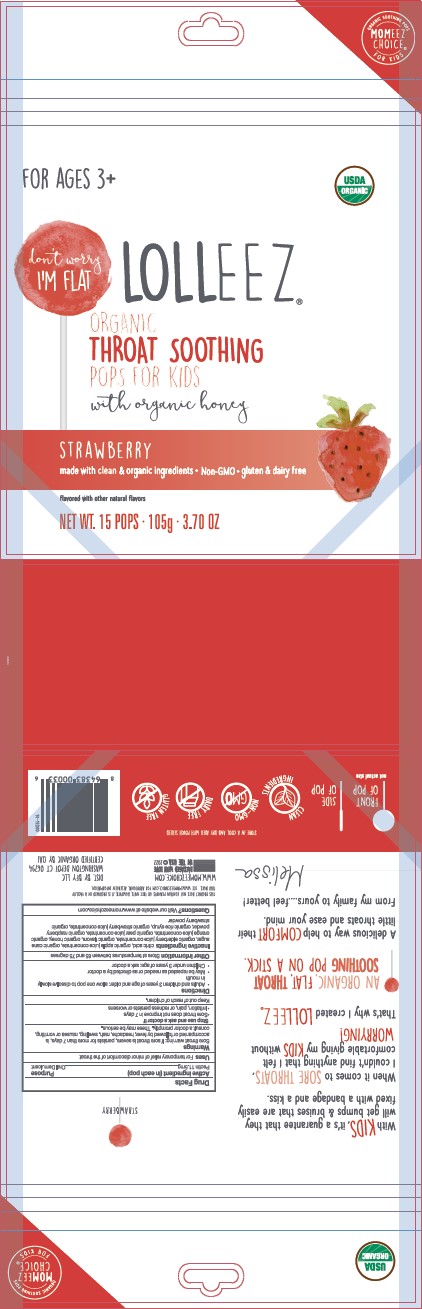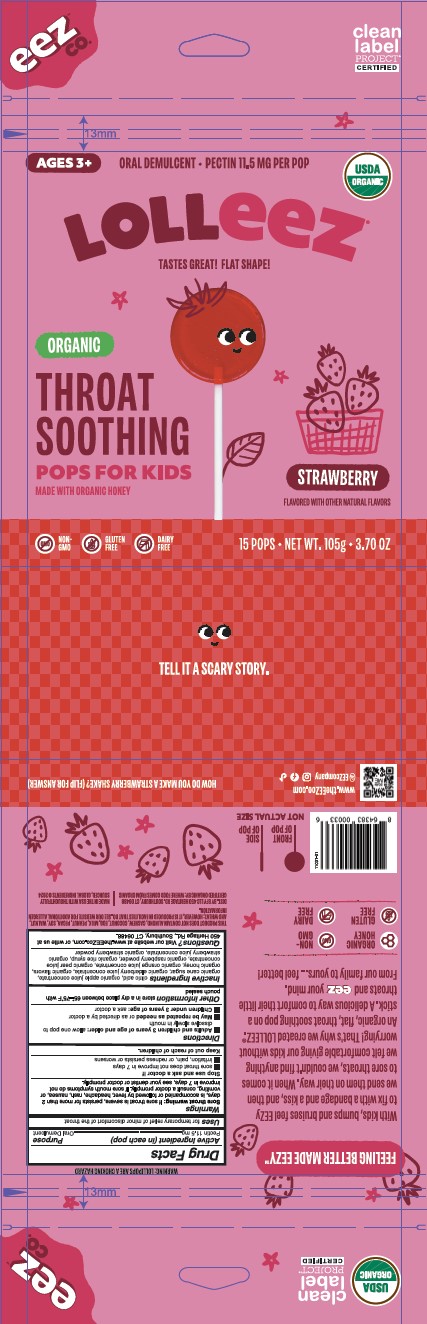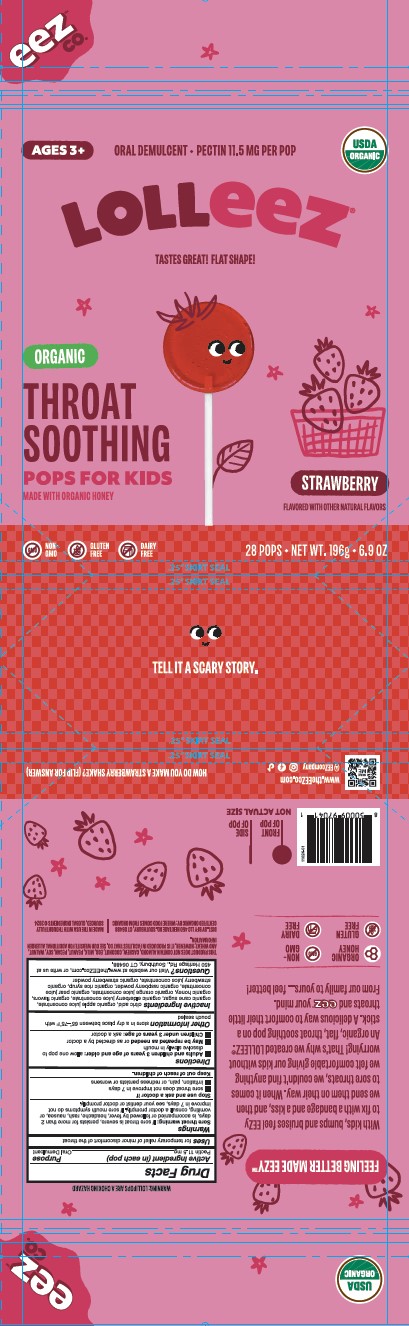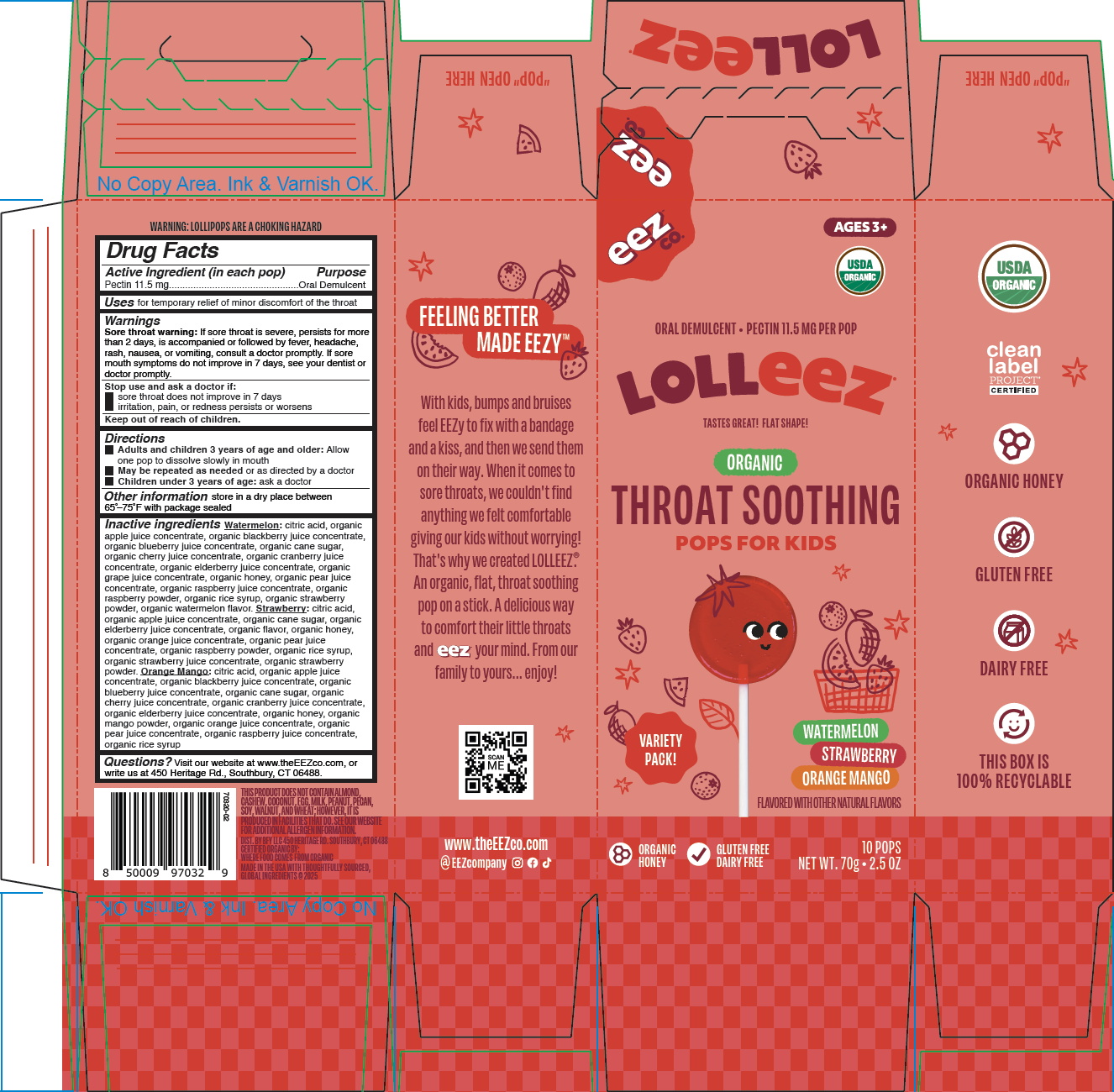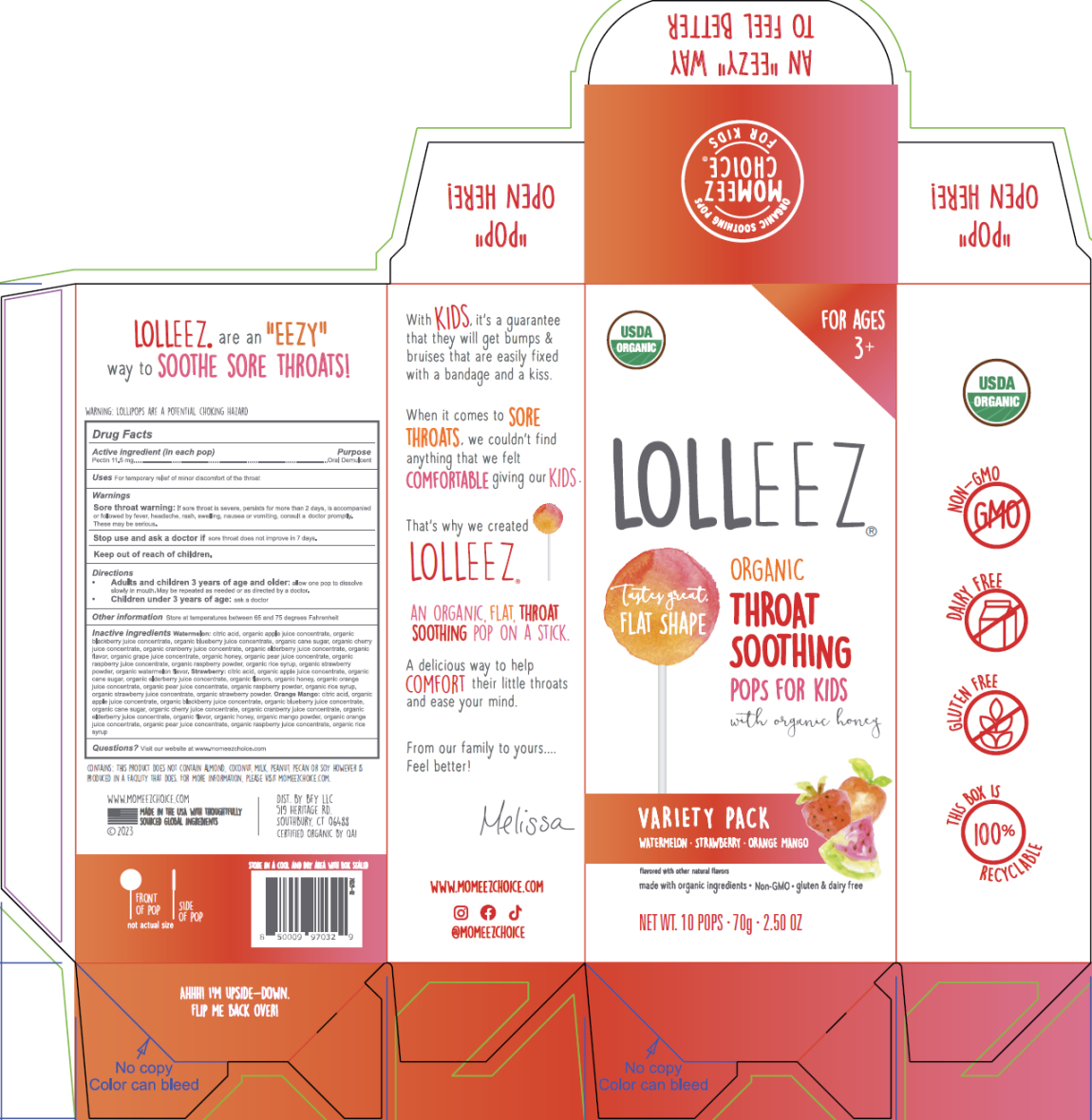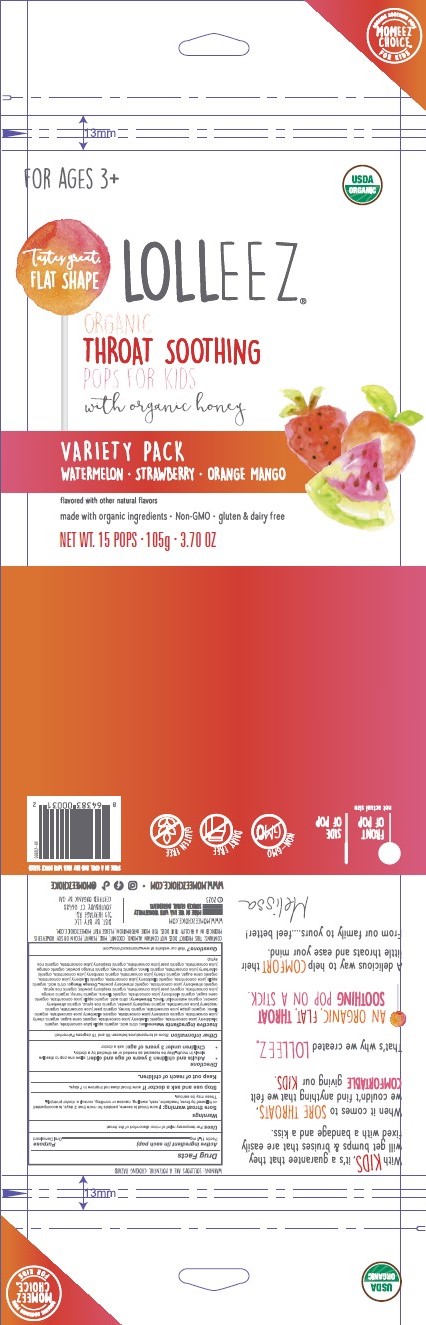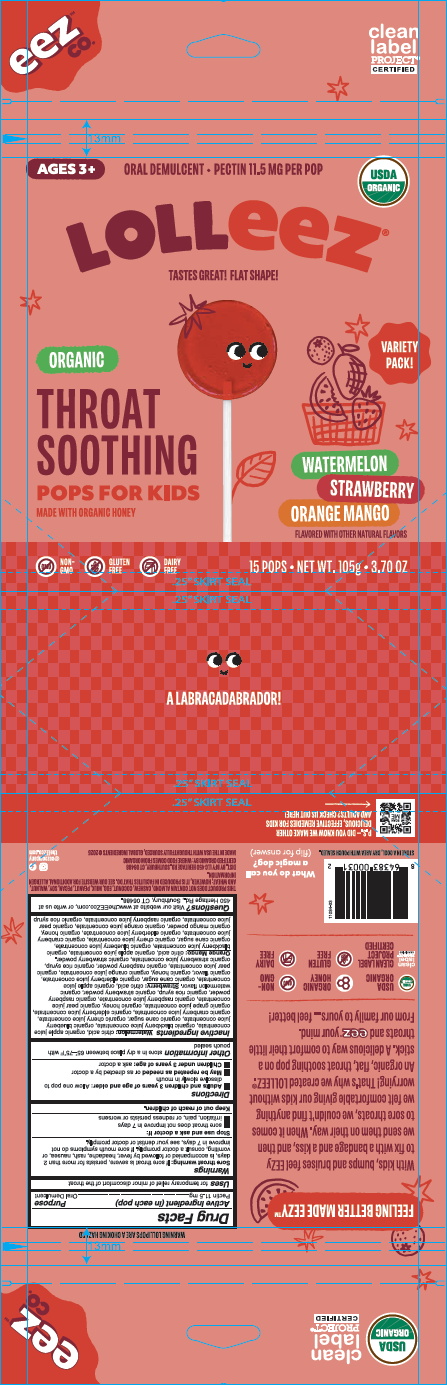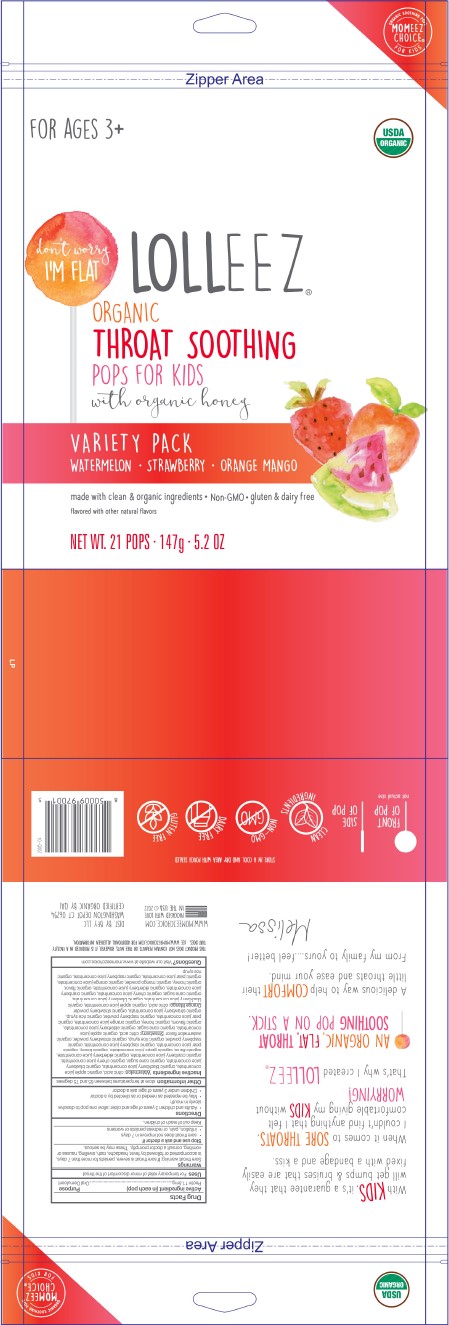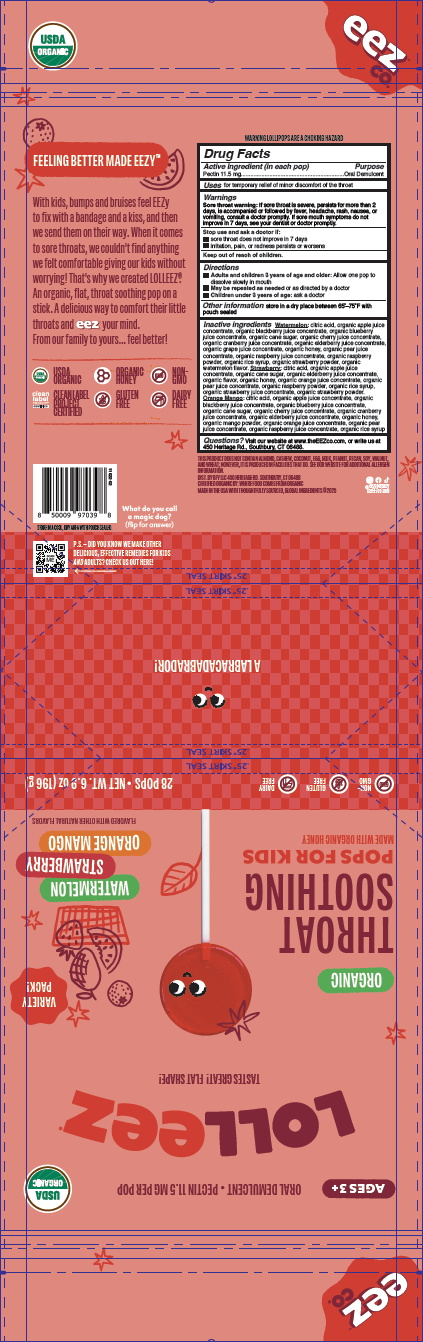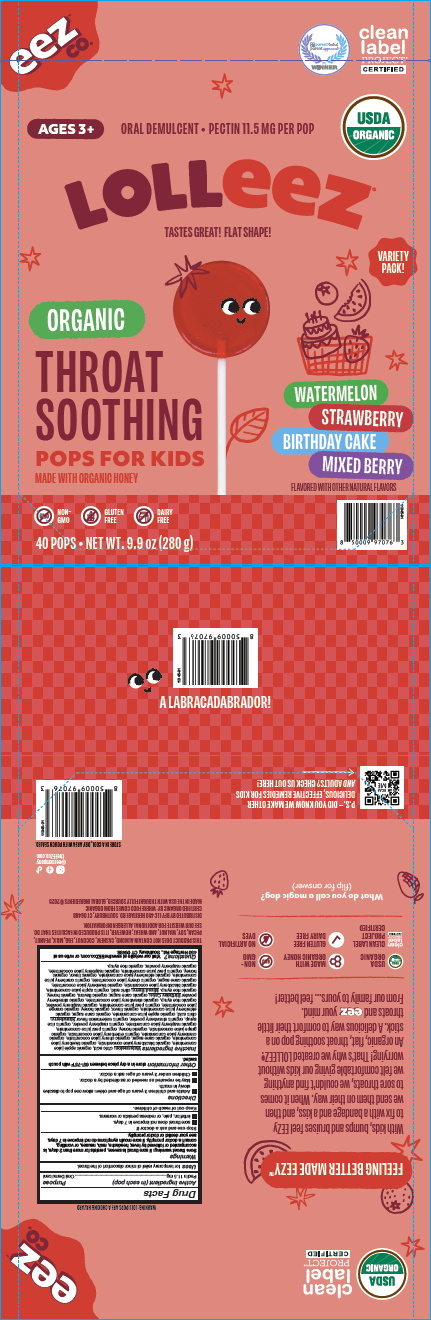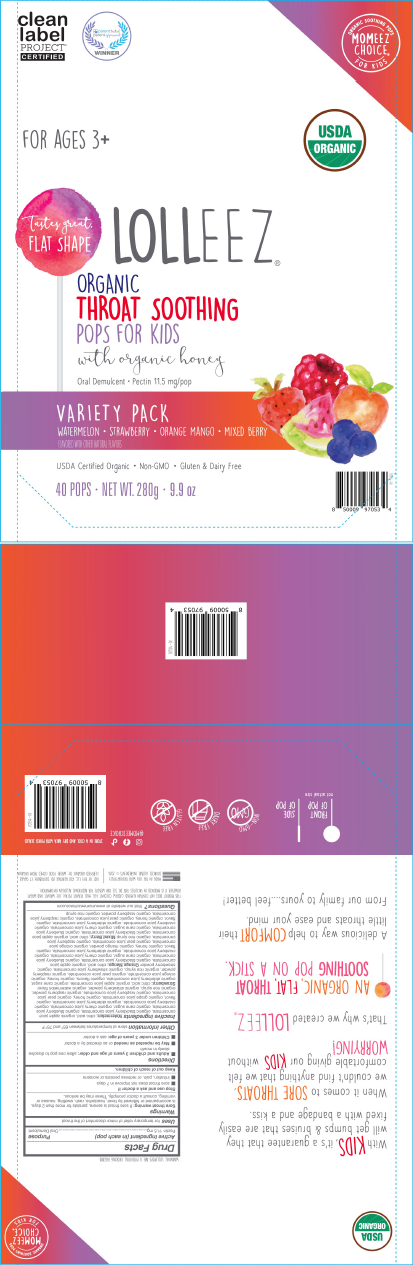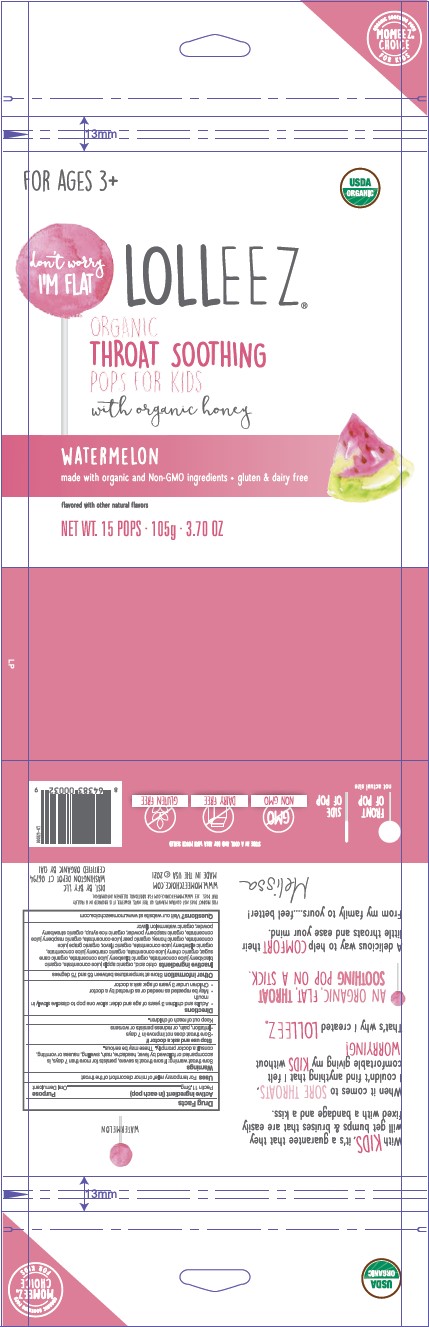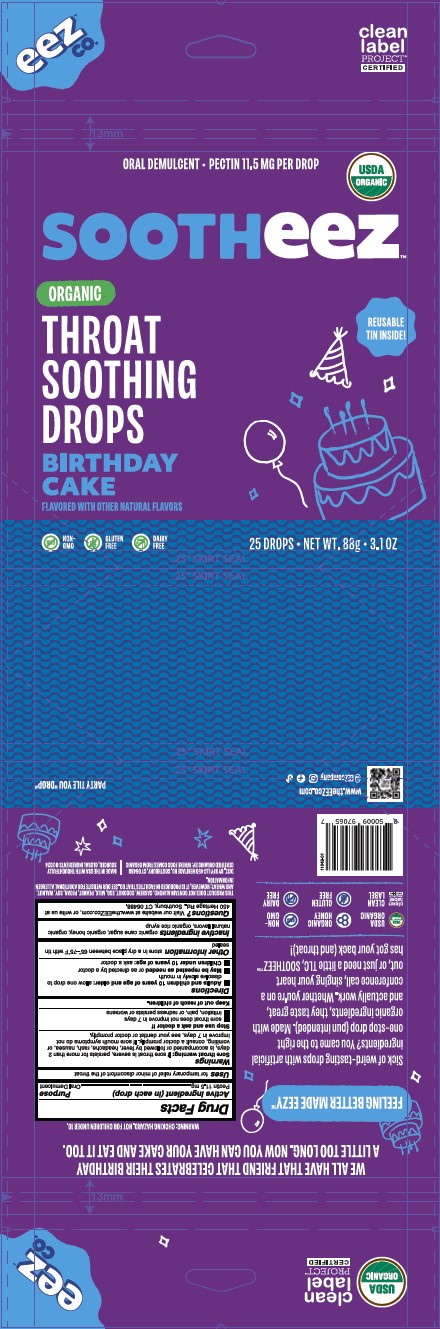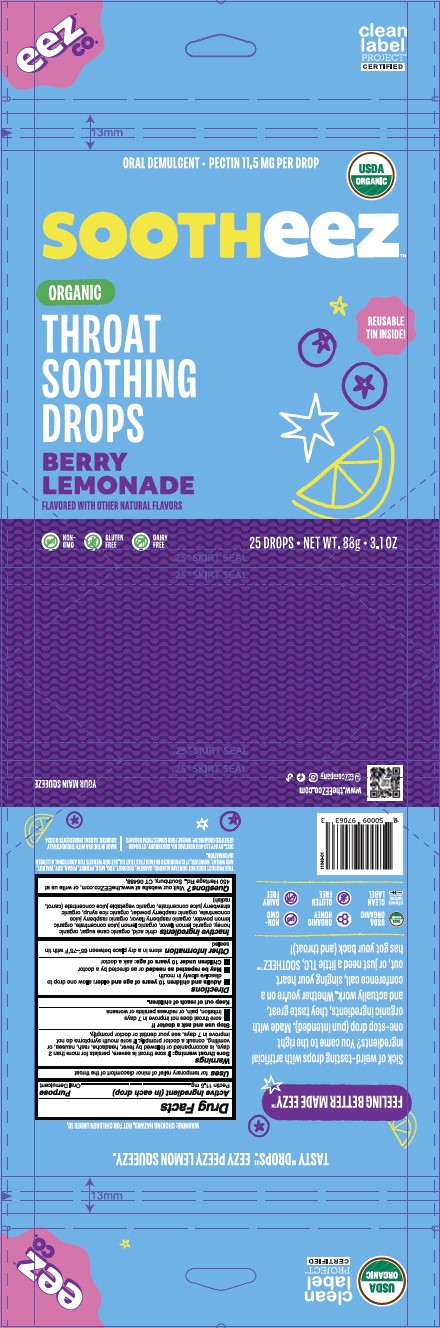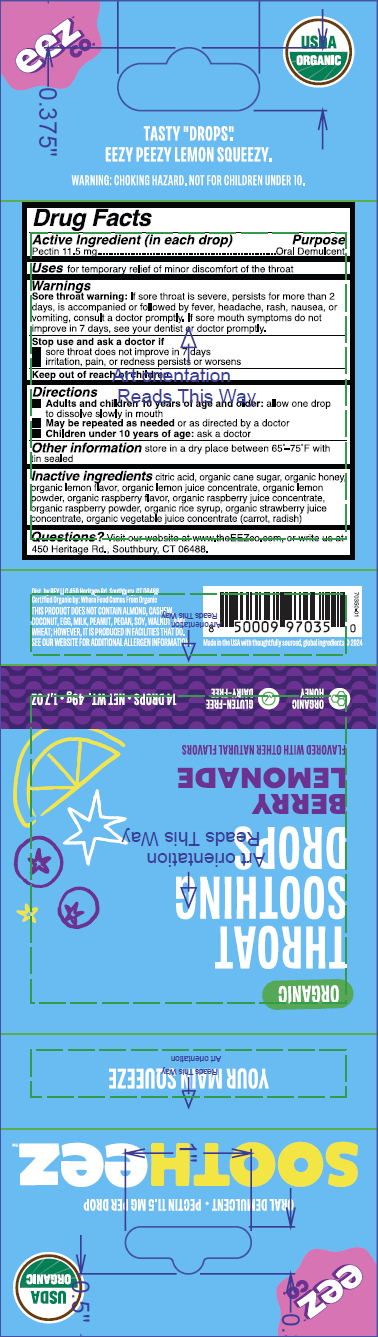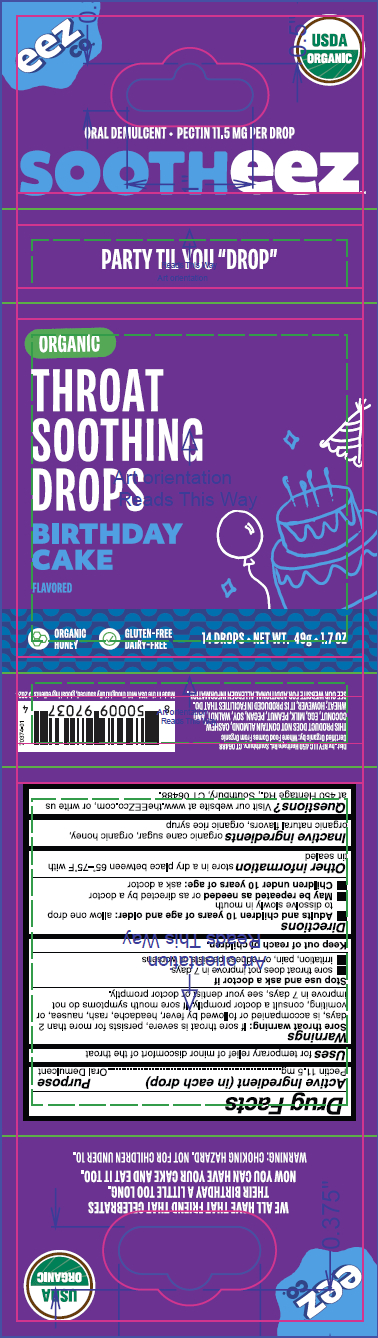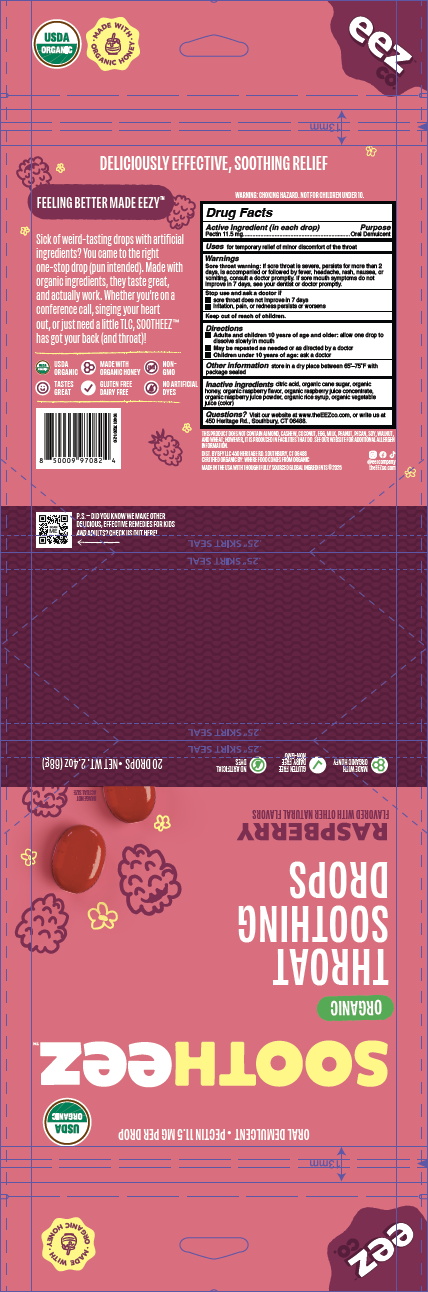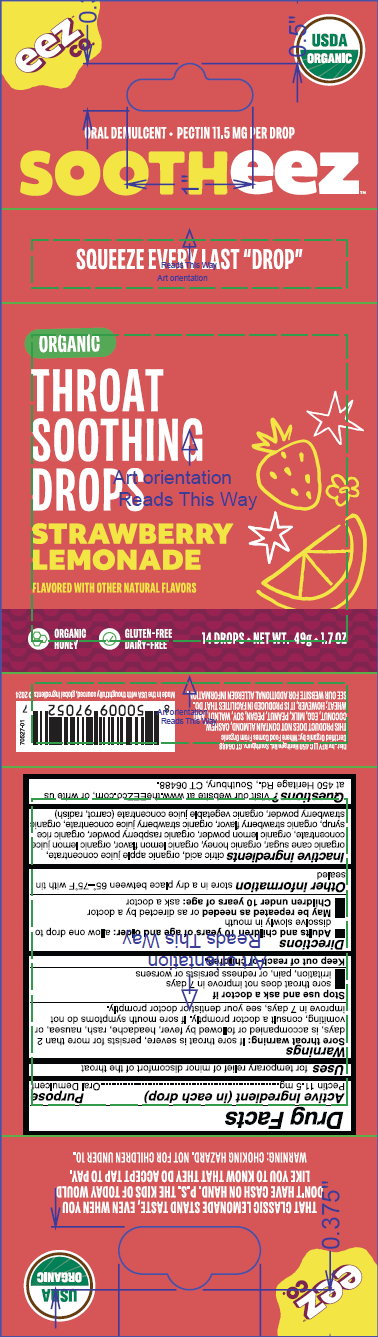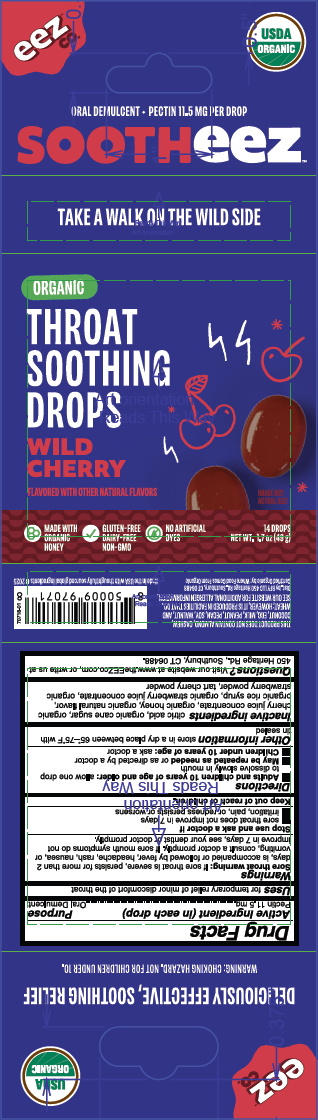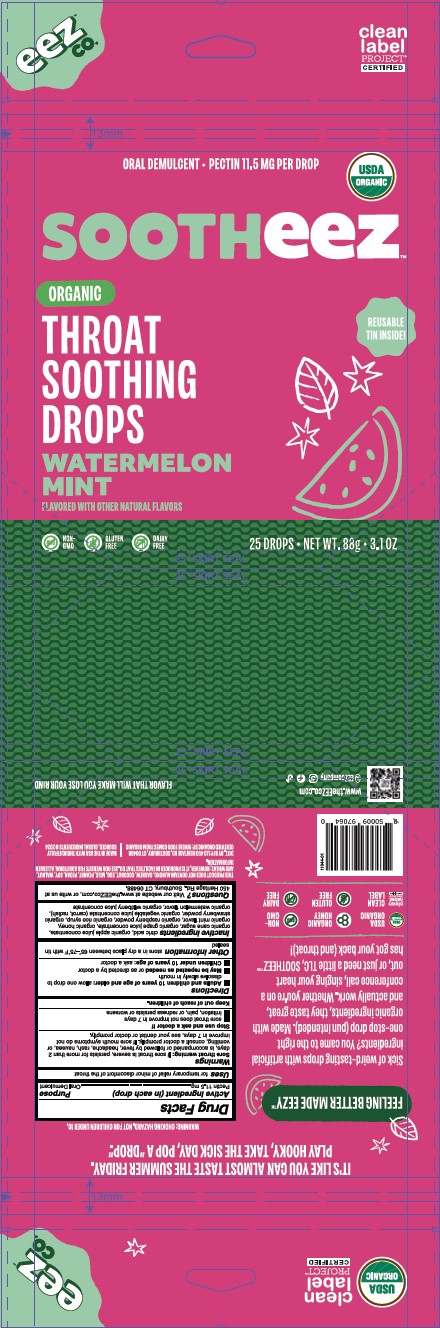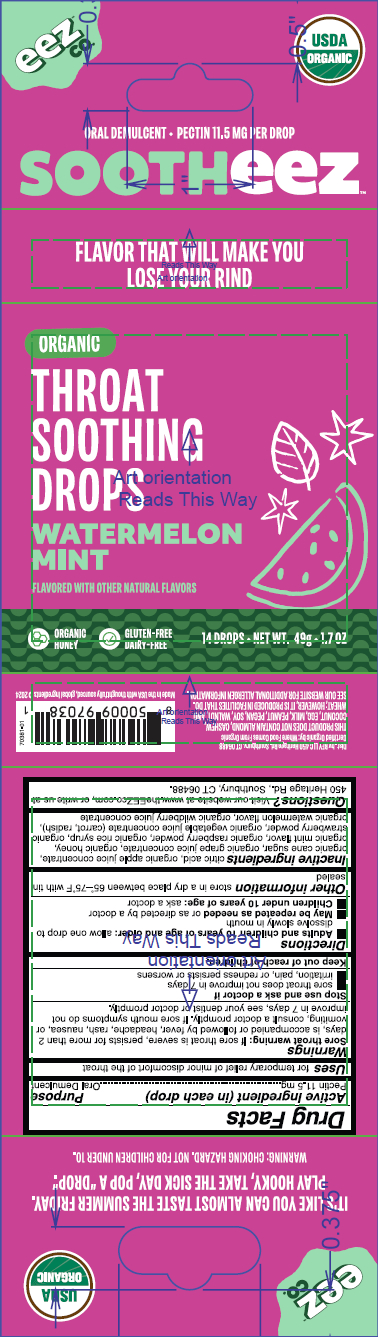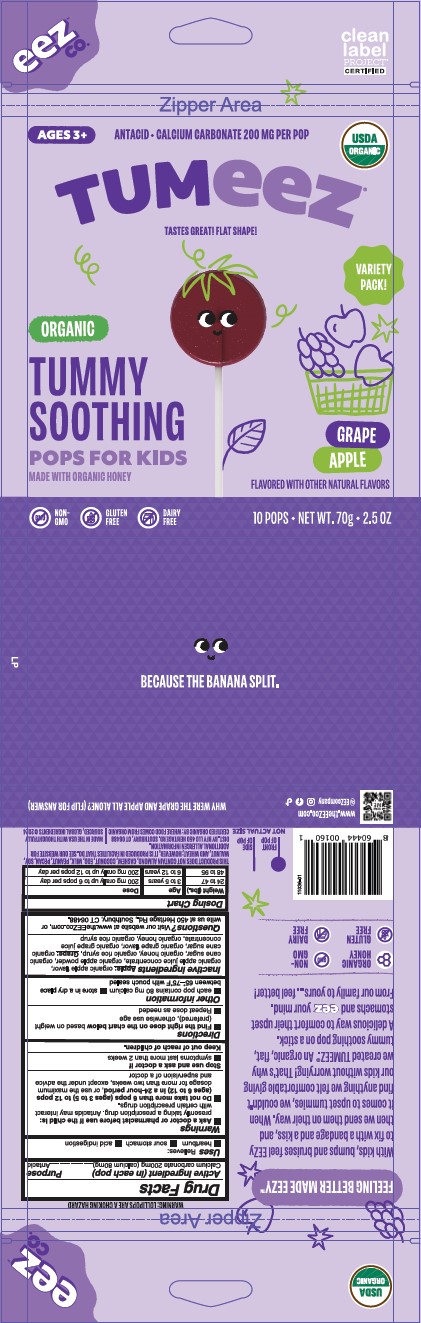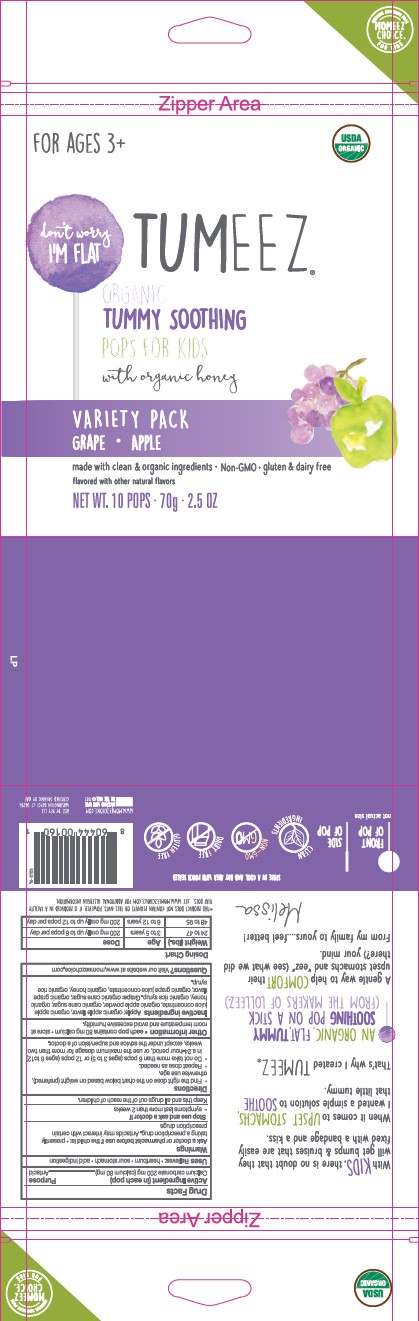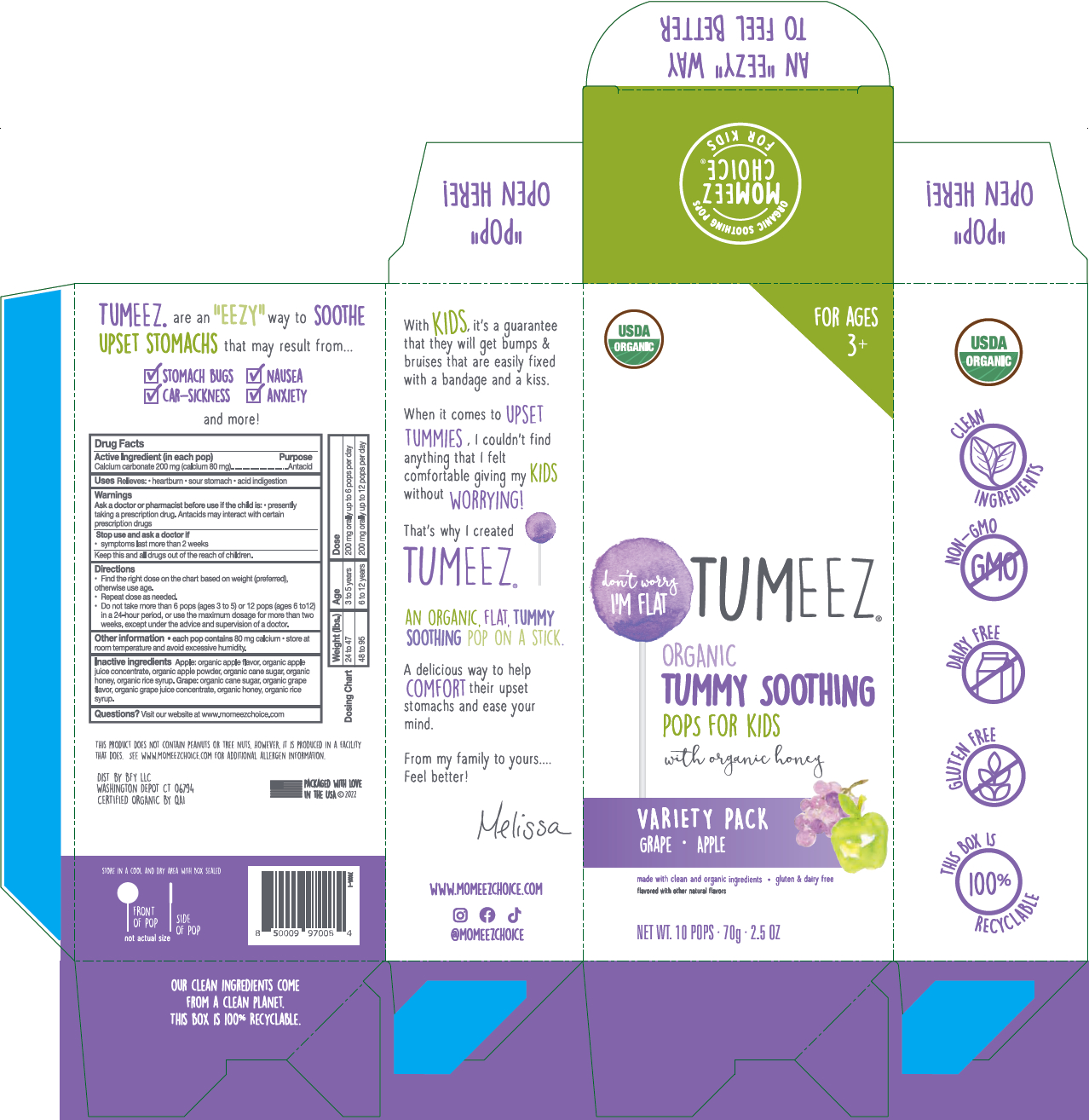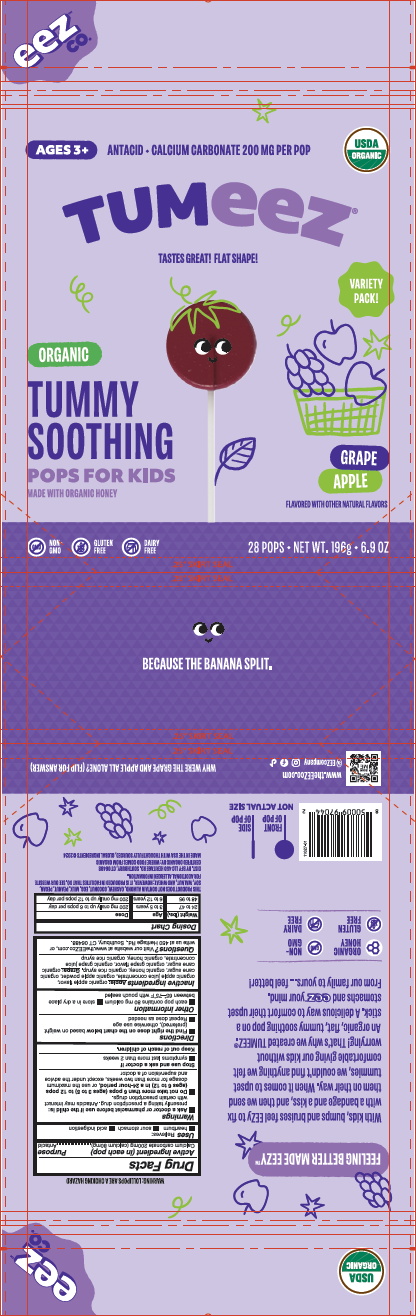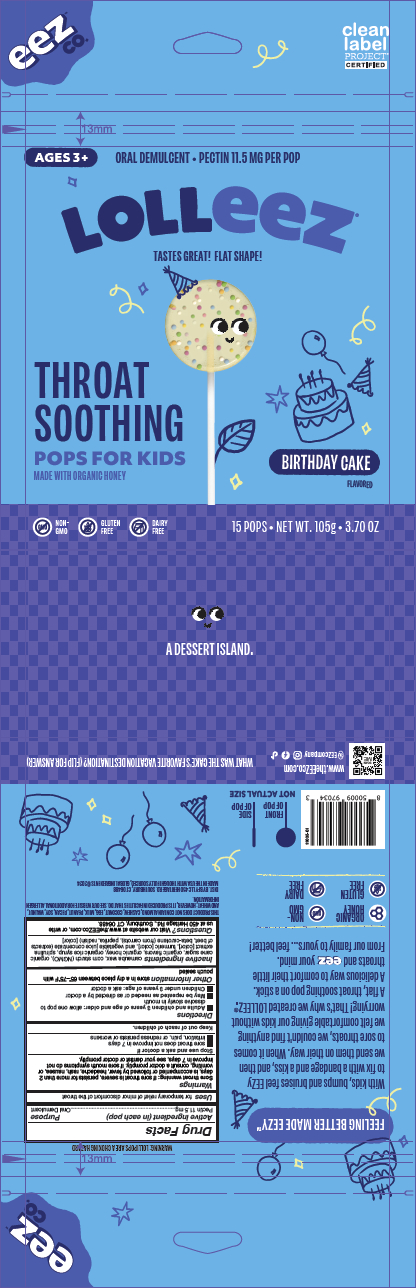 DRUG LABEL: Sootheez Organic Raspberry
NDC: 72427-3814 | Form: LOZENGE
Manufacturer: BFY LLC
Category: otc | Type: HUMAN OTC DRUG LABEL
Date: 20250617

ACTIVE INGREDIENTS: PECTIN 11.5 mg/3.5 g
INACTIVE INGREDIENTS: CITRIC ACID MONOHYDRATE

BFY LLC

Lolleez Variety Pack - Organic 3195-6

Drug Facts

Active Ingredient (in each pop)

Pectin 11.5 mg

Purpose

Oral Demulcent

Uses

for temporary relief of minor discomfort of the throat

Warnings

Sore throat warning: If sore throat is severe, persists for more than 2 days, is accompanied or followed by fever, headache, rash, nausea, or vomiting, consult a doctor promptly. If sore mouth symptoms do not improve in 7 days, see your dentist or doctor promptly.

Stop use and ask a doctor if:

- sore throat does not improve in 7 days
- irritation, pain, or redness persists or worsens

Keep out of reach of children.

Directions

- Adults and children 3 years of age and older: Allow one pop to dissolve slowly in mouth
- May be repeated as needed or as directed by a doctor
- Children under 3 years of age: ask a doctor

Other information

store in a dry place between 65°-75°F with pouch sealed

Inactive ingredients

Watermelon: citric acid, organic apple juice concentrate, organic blackberry juice concentrate, organic blueberry juice concentrate, organic cane sugar, organic cherry juice concentrate, organic cranberry juice concentrate, organic elderberry juice concentrate, organic grape juice concentrate, organic honey, organic pear juice concentrate, organic raspberry juice concentrate, organic raspberry powder, organic rice syrup, organic strawberry powder, organic watermelon flavor. Strawberry: citric acid, organic apple juice concentrate, organic cane sugar, organic elderberry juice concentrate, organic flavor, organic honey, organic orange juice concentrate, organic pear juice concentrate, organic raspberry powder, organic rice syrup, organic strawberry juice concentrate, organic strawberry powder. Orange Mango: citric acid, organic apple juice concentrate, organic blackberry juice concentrate, organic blueberry juice concentrate, organic cane sugar, organic cherry juice concentrate, organic cranberry juice concentrate, organic elderberry juice concentrate, organic honey, organic mango powder, organic orange juice concentrate, organic pear juice concentrate, organic raspberry juice concentrate, organic rice syrup

Questions?

Visit our website at www.theEEZco.com, or write us at 450 Heritage Rd., Southbury, CT 06488.

Sootheez Raspberry - Organic 3814-1

Drug Facts

Active Ingredient (in each drop)

Pectin 11.5 mg

Purpose

Oral Demulcent

Uses

for temporary relief of minor discomfort of the throat

Warnings

Sore throat warning: If sore throat is severe, persists for more than 2 days, is accompanied or followed by fever, headache, rash, nausea, or vomiting, consult a doctor promptly. If sore mouth symptoms do not improve in 7 days, see your dentist or doctor promptly.

Stop use and ask a doctor if

- sore throat does not improve in 7 days
- irritation, pain, or redness persists or worsens

Keep out of reach of children.

Directions

- Adults and children 10 years of age and older: allow one drop to dissolve slowly in mouth
- May be repeated as needed or as directed by a doctor
- Children under 10 years of age: ask a doctor

Other information

store in a dry place between 65°-75°F with package sealed

Inactive ingredients

citric acid, organic cane sugar, organic honey, organic raspberry flavor, organic raspberry juice concentrate, organic raspberry juice powder, organic rice syrup, organic vegetable juice (color)

Questions?

Visit our website at www.theEEZco.com, or write us at 450 Heritage Rd., Southbury, CT 06488.

Sootheez Wild Cherry - Organic 3714-1

Drug Facts

Active Ingredient (in each drop)

Pectin 11.5 mg

Purpose

Oral Demulcent

Uses

for temporary relief of minor discomfort of the throat

Warnings

Sore throat warning: if sore throat is severe, persists for more than 2 days, is accompanied or followed by fever, headache, rash, nausea, or vomiting, consult a doctor promptly. If sore mouth symptoms do not improve in 7 days, see your dentist or doctor promptly.

Stop use and ask a doctor if

- sore throat does not improve in 7 days
- irritation, pain, or redness persists or worsens

Keep out of reach of children.

Directions

- Adults and children 10 years of age and older: allow one drop to dissolve slowly in mouth
- May be repeated as needed or as directed by a doctor
- Children under 10 years of age: ask a doctor

Other information

store in a dry place between 65° - 75°F with tin sealed

Inactive ingredients

citric acid, organic cane sugar, organic cherry juice concentrate, organic honey, organic natural flavor, organic rice syrup, organic strawberry juice concentrate, organic strawberry powder, tart cherry powder

Questions?

Visit our website at www.theEEZco.com, or write us at 450 Heritage Rd., Southbury, CT 06488.

Lolleez Variety Pack - Organic (WM, SB, BC, MB) 3640-1

Drug Facts

Active ingredient (in each pop)

Pectin 11.5 mg

Purpose

Oral Demulcent

Uses

for temporary relief of minor discomfort of the throat.

Warnings

Sore throat warning: If sore throat is severe, persists for more than 2 days, is accompanied or followed by fever, headache, rash, nausea, or vomiting, consult a doctor promptly. If sore mouth symptoms do not improve in 7 days, see your dentist or doctor promptly.

Stop use and ask a doctor if

- sore throat does not improve in 7 days.
- irritation, pain, or redness persists or worsens.

Keep out of reach of children.

Directions

- Adults and children 3 years of age and older: allow one pop to dissolve slowly in mouth.
- May be repeated as needed or as directed by a doctor.
- Children under 3 years of age: ask a doctor.

Other Information

store in a dry place between 65°-75°F with pouch sealed.

Inactive ingredients

Watermelon: citric acid, organic apple juice concentrate, organic blackberry juice concentrate, organic blueberry juice concentrate, organic cane sugar, organic cherry juice concentrate, organic cranberry juice concentrate, organic elderberry juice concentrate, organic grape juice concentrate, organic honey, organic pear juice concentrate, organic raspberry juice concentrate, organic raspberry powder, organic rice syrup, organic strawberry powder, organic watermelon flavor Strawberry: citric acid, organic apple juice concentrate, organic cane sugar, organic elderberry juice concentrate, organic flavor, organic honey, organic orange juice concentrate, organic pear juice concentrate, organic raspberry powder, organic rice syrup, organic strawberry juice concentrate, organic strawberry powder Birthday Cake: organic cane sugar, organic flavors, organic honey, organic rice syrup. Mixed Berry: citric acid, organic apple juice concentrate, organic blackberry juice concentrate, organic blueberry juice concentrate, organic cane sugar, organic cherry juice concentrate, organic cranberry juice concentrate, organic elderberry juice concentrate, organic flavor, organic honey, organic pear juice concentrate, organic raspberry juice concentrate, organic raspberry powder, organic rice syrup.

Questions?

Visit our website at www.theEEZco.com, or write us at 450 Heritage Rd., Southbury, CT 06488.

Lolleez Variety Pack - Organic 3195-1

Drug Facts

Active ingredient (in each pop)

Pectin 11.5 mg

Purpose

Oral Demulcent

Uses

For temporary relief of minor discomfort of the throat

Warnings

Sore throat warning: If sore throat is severe, persists for more than 2 days, is accompanied or followed by fever, headache, rash, swelling, nausea or vomiting, consult a doctor promptly. These may be serious.

Stop use and ask a doctor if sore throat does not improve in 7 days

Keep out of reach of children.

Directions

- Adults and children 3 years of age and older: allow one pop to dissolve slowly in mouth. May be repeated as needed or as directed by a doctor.
- Children under 3 years of age: ask a doctor

Other information

Store at temperatures between 65 and 75 degrees Fahrenheit

Inactive ingredients

Watermelon: citric acid, organic apple juice concentrate, organic blackberry juice concentrate, organic blueberry juice concentrate, organic cane sugar, organic cherry juice concentrate, organic cranberry juice concentrate, organic elderberry juice concentrate, organic flavor, organic grape juice concentrate, organic honey, organic pear juice concentrate, organic raspberry juice concentrate, organic raspberry powder, organic rice syrup, organic strawberry powder, organic watermelon flavor. Strawberry: citric acid, organic apple juice concentrate, organic cane sugar, organic elderberry juice concentrate, organic flavors, organic honey, organic orange juice concentrate, organic pear juice concentrate, organic raspberry powder, organic rice syrup, organic strawberry juice concentrate, organic strawberry powder. Orange Mango: citric acid, organic apple juice concentrate, organic blackberry juice concentrate, organic blueberry juice concentrate, organic cane sugar, organic cherry juice concentrate, organic cranberry juice concentrate, organic elderberry juice concentrate, organic flavor, organic honey, organic mango powder, organic orange juice concentrate, organic pear juice concentrate, organic raspberry juice concentrate, organic rice syrup.

Questions?

Visit our website at www.momeezchoice.com

Lolleez Variety Pack - Organic 3195-2

Drug Facts

Active ingredient (in each pop)

Pectin 11.5 mg

Purpose

Oral Demulcent

Uses

For temporary relief of minor discomfort of the throat

Warnings

Sore throat warning: If sore throat is severe, persists for more than 7 days, is accompanied or followed by fever, headache, rash, swelling, nausea or vomiting, consult a doctor promptly. These may be serious.

Stop use and ask a doctor if

- sore throat does not improve in 7 days
- irritation, pain, or redness persists or worsens

Keep out of reach of children.

Directions

- Adults and children 3 years of age and older: allow one pop to dissolve slowly in mouth
- May be repeated as needed or as directed by a doctor
- Children under 3 years of age: ask a doctor

Other information

store at temperatures between 65 and 75 degrees

Inactive ingredients

Watermelon: citric acid, organic apple juice concentrate, organic blackberry juice concentrate, organic blueberry juice concentrate, organic cane sugar, organic cherry juice concentrate, organic cranberry juice concentrate, organic elderberry juice concentrate, organic flavor, organic grape juice concentrate, organic honey, organic pear juice concentrate, organic raspberry juice concentrate, organic raspberry powder, organic rice syrup, organic strawberry powder, organic watermelon flavor. Strawberry: citric acid, organic apple juice concentrate, organic cane sugar, organic elderberry juice concentrate, organic flavors, organic honey, organic orange juice concentrate, organic pear juice concentrate, organic raspberry powder, organic rice syrup, organic strawberry juice concentrate, organic strawberry powder. Orange Mango: citric acid, organic apple juice concentrate, organic blackberry juice concentrate, organic blueberry juice concentrate, organic cane sugar, organic cherry juice concentrate, organic cranberry juice concentrate, organic elderberry juice concentrate, organic flavor, organic honey, organic mango powder, organic orange juice concentrate, organic pear juice concentrate, organic raspberry juice concentrate, organic rice syrup

Questions?

Visit our website at www.momeezchoice.com

Lolleez Variety Pack - Organic 3195-3

Drug Facts

Active ingredient (in each pop)

Pectin 11.5 mg

Purpose

Oral Demulcent

Uses

For temporary relief of minor discomfort of the throat

Warnings

Sore throat warning: If sore throat is severe, persists for more than 2 days, is accompanied or followed by fever, headache, rash, swelling, nausea or vomiting, consult a doctor promptly. These may be serious.

Stop use and ask a doctor if sore throat does not improve in 7 days.

Keep out of reach of children.

Directions

- Adults and children 3 years of age and older: allow one pop to dissolve slowly in mouth. May be repeated as needed or as directed by a doctor.
- Children under 3 years of age: ask a doctor

Other information

Store at temperatures between 65 and 75 degrees Fahrenheit

Inactive ingredients

Watermelon: citric acid, organic apple juice concentrate, organic blackberry juice concentrate, organic blueberry juice concentrate, organic cane sugar, organic cherry juice concentrate, organic cranberry juice concentrate, organic elderberry juice concentrate, organic flavor, organic grape juice concentrate, organic honey, organic pear juice concentrate, organic raspberry juice concentrate, organic raspberry powder, organic rice syrup, organic strawberry powder, organic watermelon flavor. Strawberry: citric acid, organic apple juice concentrate, organic cane sugar, organic elderberry juice concentrate, organic flavors, organic honey, organic orange juice concentrate, organic pear juice concentrate, organic raspberry powder, organic rice syrup, organic strawberry juice concentrate, organic strawberry powder. Orange Mango: citric acid, organic apple juice concentrate, organic blackberry juice concentrate, organic blueberry juice concentrate, organic cane sugar, organic cherry juice concentrate, organic cranberry juice concentrate, organic elderberry juice concentrate, organic flavor, organic honey, organic mango powder, organic orange juice concentrate, organic pear juice concentrate, organic raspberry juice concentrate, organic rice syrup

Questions?

Visit our website at www.momeezchoice.com

Lolleez Variety Pack - Organic 3195-4

Drug Facts

Active Ingredient (in each pop)

Pectin 11.5 mg

Purpose

Oral Demulcent

Uses

for temporary relief of minor discomfort of the throat

Warnings

Sore throat warning: If sore throat is severe, persists for more than 2 days, is accompanied or followed by fever, headache, rash, nausea, or vomiting, consult a doctor promptly. If sore mouth symptoms do not improve in 7 days, see your dentist or doctor promptly.

Stop use and ask a doctor if:

- sore throat does not improve in 7 days
- irritation, pain, or redness persists or worsens

Keep out of reach of children.

Directions

- Adults and children 3 years of age and older: Allow one pop to dissolve slowly in mouth
- May be repeated as needed or as directed by a doctor
- Children under 3 years of age: ask a doctor

Other information

store in a dry place between 65°-75°F with package sealed

Inactive ingredients

Watermelon: citric acid, organic apple juice concentrate, organic blackberry juice concentrate, organic blueberry juice concentrate, organic cane sugar, organic cherry juice concentrate, organic cranberry juice concentrate, organic elderberry juice concentrate, organic grape juice concentrate, organic honey, organic pear juice concentrate, organic raspberry juice concentrate, organic raspberry powder, organic rice syrup, organic strawberry powder, organic watermelon flavor. Strawberry: citric acid, organic apple juice concentrate, organic cane sugar, organic elderberry juice concentrate, organic flavor, organic honey, organic orange juice concentrate, organic pear juice concentrate, organic raspberry powder, organic rice syrup, organic strawberry juice concentrate, organic strawberry powder. Orange Mango: citric acid, organic apple juice concentrate, organic blackberry juice concentrate, organic blueberry juice concentrate, organic cane sugar, organic cherry juice concentrate, organic cranberry juice concentrate, organic elderberry juice concentrate, organic honey, organic mango powder, organic orange juice concentrate, organic pear juice concentrate, organic raspberry juice concentrate, organic rice syrup

Questions?

Visit our website at www.theEEZco.com, or write us at 450 Heritage Rd., Southbury, CT 06488.

Lolleez Variety Pack - Organic 3195-5

Drug Facts

Active Ingredient (in each pop)

Pectin 11.5 mg

Purpose

Oral Demulcent

Uses

for temporary relief of minor discomfort of the throat

Warnings

Sore throat warning: If sore throat is severe, persists for more than 2 days, is accompanied or followed by fever, headache, rash, nausea, or vomiting, consult a doctor promptly. If sore mouth symptoms do not improve in 7 days, see your dentist or doctor promptly.

Stop use and ask a doctor if:

- sore throat does not improve in 7 days
- irritation, pain, or redness persists or worsens

Keep out of reach of children.

Directions

- Adults and children 3 years of age and older: Allow one pop to dissolve slowly in mouth
- May be repeated as needed or as directed by a doctor
- Children under 3 years of age: ask a doctor

Other information

store in a dry place between 65°-75°F with pouch sealed

Inactive ingredients

Watermelon: citric acid, organic apple juice concentrate, organic blackberry juice concentrate, organic blueberry juice concentrate, organic cane sugar, organic cherry juice concentrate, organic cranberry juice concentrate, organic elderberry juice concentrate, organic grape juice concentrate, organic honey, organic pear juice concentrate, organic raspberry juice concentrate, organic raspberry powder, organic rice syrup, organic strawberry powder, organic watermelon flavor. Strawberry: citric acid, organic apple juice concentrate, organic cane sugar, organic elderberry juice concentrate, organic flavor, organic honey, organic orange juice concentrate, organic pear juice concentrate, organic raspberry powder, organic rice syrup, organic strawberry juice concentrate, organic strawberry powder. Orange Mango: citric acid, organic apple juice concentrate, organic blackberry juice concentrate, organic blueberry juice concentrate, organic cane sugar, organic cherry juice concentrate, organic cranberry juice concentrate, organic elderberry juice concentrate, organic honey, organic mango powder, organic orange juice concentrate, organic pear juice concentrate, organic raspberry juice concentrate, organic rice syrup

Questions?

Visit our website at www.theEEZco.com, or write us at 450 Heritage Rd., Southbury, CT 06488.

Lolleez Variety Pack (MB-OM-SB-WM) - Organic 4540-1

Drug Facts

Active Ingredient (in each pop)

Pectin 11.5 mg

Purpose

Oral Demulcent

Uses

for temporary relief of minor discomfort of the throat

Warnings

Sore throat warning: If sore throat is severe, persists for more than 2 days, is accompanied or followed by fever, headache, rash, swelling, nausea or vomiting, consult a doctor promptly. These may be serious.

Stop use and ask a doctor if

- sore throat does not improve in 7 days
- irritation, pain, or redness persists or worsens

Keep out of reach of children.

Directions

- Adults and children 3 years of age and older: allow one pop to dissolve slowly in mouth
- May be repeated as needed or as directed by a doctor
- Children under 3 years of age: ask a doctor

Other information

store at temperatures between 65° and 75°F

Inactive ingredients

Watermelon: citric acid, organic apple juice concentrate, organic blackberry juice concentrate, organic blueberry juice concentrate, organic cane sugar, organic cherry juice concentrate, organic cranberry juice concentrate, organic elderberry juice concentrate, organic flavor, organic grape juice concentrate, organic honey, organic pear juice concentrate, organic raspberry juice concentrate, organic raspberry powder, organic rice syrup, organic strawberry powder, organic watermelon flavor Strawberry: citric acid, organic apple juice concentrate, organic cane sugar, organic elderberry juice concentrate, organic flavors, organic honey, organic orange juice concentrate, organic pear juice concentrate, organic raspberry powder, organic rice syrup, organic strawberry juice concentrate, organic strawberry powder Orange Mango: citric acid, organic apple juice concentrate, organic blackberry juice concentrate, organic blueberry juice concentrate, organic cane sugar, organic cherry juice concentrate, organic cranberry juice concentrate, organic elderberry juice concentrate, organic flavor, organic honey, organic mango powder, organic orange juice concentrate, organic pear juice concentrate, organic raspberry juice concentrate, organic rice syrup Mixed Berry: citric acid, organic apple juice concentrate, organic blackberry juice concentrate, organic blueberry juice concentrate, organic cane sugar, organic cherry juice concentrate, organic cranberry juice concentrate, organic elderberry juice concentrate, organic flavor, organic honey, organic pear juice concentrate, organic raspberry juice concentrate, organic raspberry powder, organic rice syrup

Questions?

Visit our website at www.momeezchoice.com

Lolleez Watermelon - Organic 3295-1

Drug Facts

Active ingredient (in each pop)

Pectin 11.5 mg

Purpose

Oral Demulcent

Uses

For temporary relief of minor discomfort of the throat

Warnings

Sore throat warning: If sore throat is severe, persists for more than 7 days, is accompanied or followed by fever, headache, rash, swelling, nausea or vomiting, consult a doctor promptly. These may be serious.

Stop use and ask a doctor if

- Sore throat does not improve in 7 days
- Irritation, pain, or redness persists or worsens

Keep out of reach of children.

Directions

- Adults and children 3 years of age and older: allow one pop to dissolve slowly in mouth
- May be repeated as needed or as directed by a doctor
- Children under 3 years of age: ask a doctor

Other information

Store at temperatures between 65 and 75 degrees

Inactive ingredients

citric acid, organic apple juice concentrate, organic blackberry juice concentrate, organic blueberry juice concentrate, organic cane sugar, organic cherry juice concentrate, organic cranberry juice concentrate, organic elderberry juice concentrate, organic flavor, organic grape juice concentrate, organic honey, organic pear juice concentrate, organic raspberry juice concentrate, organic raspberry powder, organic rice syrup, organic strawberry powder, organic watermelon flavor

Questions?

Visit our website at www.momeezchoice.com

Lolleez Strawberry - Organic 3395-1

Drug Facts

Active ingredient (in each pop)

Pectin 11.5 mg

Purpose

Oral Demulcent

Uses

For temporary relief of minor discomfort of the throat

Warnings

Sore throat warning: If sore throat is severe, persists for more than 7 days, is accompanied or followed by fever, headache, rash, swelling, nausea or vomiting, consult a doctor promptly. These may be serious.

Stop use and ask a doctor if

- Sore throat does not improve in 7 days
- Irritation, pain, or redness persists or worsens

Keep out of reach of children.

Directions

- Adults and children 3 years of age and older: allow one pop to dissolve slowly in mouth
- May be repeated as needed or as directed by a doctor
- Children under 3 years of age: ask a doctor

Other information

Store at temperatures between 65 and 75 degrees

Inactive ingredients

citric acid, organic apple juice concentrate, organic cane sugar, organic elderberry juice concentrate, organic flavors, organic honey, organic orange juice concentrate, organic pear juice concentrate, organic raspberry powder, organic rice syrup, organic strawberry juice concentrate, organic strawberry powder

Questions?

Visit our website at www.momeezchoice.com

Lolleez Strawberry - Organic 3395-2

Drug Facts

Active Ingredient (in each pop)

Pectin 11.5 mg

Purpose

Oral Demulcent

Uses

for temporary relief of minor discomfort of the throat

Warnings

Sore throat warning: If sore throat is severe, persists for more than 2 days, is accompanied or followed by fever, headache, rash, nausea, or vomiting, consult a doctor promptly. If sore mouth symptoms do not improve in 7 days, see your dentist or doctor promptly.

Stop use and ask a doctor if

- sore throat does not improve in 7 days
- irritation, pain, or redness persists or worsens

Keep out of reach of children.

Directions

- Adults and children 3 years of age and older: allow one pop to dissolve slowly in mouth
- May be repeated as needed or as directed by a doctor
- Children under 3 years of age: ask a doctor

Other information

store in a dry place between 65°-75°F with pouch sealed

Inactive ingredients

citric acid, organic apple juice concentrate, organic cane sugar, organic elderberry juice concentrate, organic flavors, organic honey, organic orange juice concentrate, organic pear juice concentrate, organic raspberry powder, organic rice syrup, organic strawberry juice concentrate, organic strawberry powder

Questions?

Visit our website at www.theEEZco.com, or write us at 450 Heritage Rd., Southbury, CT 06488.

Lolleez Strawberry - Organic 3395-3

Drug Facts

Active Ingredient (in each pop)

Pectin 11.5 mg

Purpose

Oral Demulcent

Uses

for temporary relief of minor discomfort of the throat

Warnings

Sore throat warning: If sore throat is severe, persists for more than 2 days, is accompanied or followed by fever, headache, rash, nausea, or vomiting, consult a doctor promptly. If sore mouth symptoms do not improve in 7 days, see your dentist or doctor promptly.

Stop use and ask a doctor if

- sore throat does not improve in 7 days
- irritation, pain, or redness persists or worsens

Keep out of reach of children.

Directions

- Adults and children 3 years of age and older: allow one pop to dissolve slowly in mouth
- May be repeated as needed or as directed by a doctor
- Children under 3 years of age: ask a doctor

Other information

store in a dry place between 65°-75°F with pouch sealed

Inactive ingredients

citric acid, organic apple juice concentrate, organic cane sugar, organic elderberry juice concentrate, organic flavors, organic honey, organic orange juice concentrate, organic pear juice concentrate, organic raspberry powder, organic rice syrup, organic strawberry juice concentrate, organic strawberry powder

Questions?

Visit our website at www.theEEZco.com, or write us at 450 Heritage Rd., Southbury, CT 06488.

Lolleez Orange Mango - Organic 3495-1

Drug Facts

Active ingredient (in each pop)

Pectin 11.5 mg

Purpose

Oral Demulcent

Uses

For temporary relief of minor discomfort of the throat

Warnings

Sore throat warning: if sore throat is severe, persists for more than 7 days, is accompanied or followed by fever, headache, rash, swelling, nausea or vomiting, consult a doctor promptly. These may be serious.

Stop use and ask a doctor if

- sore throat does not improve in 7 days
- irritation, pain, or redness persists or worsens

Keep out of reach of children.

Directions

- adults and children 3 years of age and older: allow one pop to dissolve slowly in mouth
- May be repeated as needed or as directed by a doctor
- Children under 3 years of age: ask a doctor

Other information

store at temperatures between 65 and 75 degrees

Inactive ingredients

Citric acid, organic apple juice concentrate, organic blackberry juice concentrate, organic blueberry juice concentrate, organic cane sugar, organic cherry juice concentrate, organic cranberry juice concentrate, organic elderberry juice concentrate, organic flavor, organic honey, organic mango powder, organic orange juice concentrate, organic pear juice concentrate, organic raspberry juice concentrate, organic rice syrup

Lolleez Mixed Berry - Organic 3515-1

Drug Facts

Active ingredient (in each pop)

Pectin 11.5 mg

Purpose

Oral Demulcent

Uses

For temporary relief of minor discomfort of the throat

Warnings

Sore throat warning: If sore throat is severe, persists for more than 2 days, is accompanied or followed by fever, headache, rash, swelling, nausea or vomiting, consult a doctor promptly. These may be serious.

Stop use and ask a doctor if sore throat does not improve in 7 days

Keep out of reach of children.

Directions

- Adults and children 3 years of age and older: allow one pop to dissolve slowly in mouth. May be repeated as needed or as directed by a doctor.
- Children under 3 years of age: ask a doctor

Other information

Store at temperatures between 65 and 75 degrees Fahrenheit

Inactive ingredients

citric acid, organic apple juice concentrate, organic blackberry juice concentrate, organic blueberry juice concentrate, organic cane sugar, organic cherry juice concentrate, organic cranberry juice concentrate, organic elderberry juice concentrate, organic flavor, organic honey, organic pear juice concentrate, organic raspberry juice concentrate, organic raspberry powder, organic rice syrup

Questions?

Visit our website at www.momeezchoice.com

Lolleez Mixed Berry - Organic 3515-2

Drug Facts

Active Ingredient (in each pop)

Pectin 11.5 mg

Purpose

Oral Demulcent

Uses

for temporary relief of minor discomfort of the throat

Warnings

Sore throat warning: If sore throat is severe, persists for more than 2 days, is accompanied or followed by fever, headache, rash, nausea, or vomiting, consult a doctor promptly. If sore mouth symptoms do not improve in 7 days, see your dentist or doctor promptly.

Stop use and ask a doctor if

- sore throat does not improve in 7 days
- irritation, pain, or redness persists or worsens

Keep out of reach of children.

Directions

- Adults and children 3 years of age and older: allow one pop to dissolve slowly in mouth
- May be repeated as needed or as directed by a doctor
- Children under 3 years of age: ask a doctor

Other information

store in a dry place between 65°-75°F with pouch sealed

Inactive ingredients

citric acid, organic apple juice concentrate, organic blackberry juice concentrate, organic blueberry juice concentrate, organic cane sugar, organic cherry juice concentrate, organic cranberry juice concentrate, organic elderberry juice concentrate, organic flavor, organic honey, organic pear juice concentrate, organic raspberry juice concentrate, organic raspberry powder, organic rice syrup

Questions?

Visit our website at www.theEEZco.com, or write us at 450 Heritage Rd., Southbury, CT 06488.

Lolleez Mixed Berry - Organic 3515-3

Drug Facts

Active Ingredient (in each pop)

Pectin 11.5 mg

Purpose

Oral Demulcent

Uses

for temporary relief of minor discomfort of the throat

Warnings

Sore throat warning: If sore throat is severe, persists for more than 2 days, is accompanied or followed by fever, headache, rash, nausea, or vomiting, consult a doctor promptly. If sore mouth symptoms do not improve in 7 days, see your dentist or doctor promptly.

Stop use and ask a doctor if

- sore throat does not improve in 7 days
- irritation, pain, or redness persists or worsens

Keep out of reach of children.

Directions

- Adults and children 3 years of age and older: allow one pop to dissolve slowly in mouth
- May be repeated as needed or as directed by a doctor
- Children under 3 years of age: ask a doctor

Other information

store in a dry place between 65°-75°F with pouch sealed

Inactive ingredients

citric acid, organic apple juice concentrate, organic blackberry juice concentrate, organic blueberry juice concentrate, organic cane sugar, organic cherry juice concentrate, organic cranberry juice concentrate, organic elderberry juice concentrate, organic flavor, organic honey, organic pear juice concentrate, organic raspberry juice concentrate, organic raspberry powder, organic rice syrup

Questions?

Visit our website at www.theEEZco.com, or write us at 450 Heritage Rd., Southbury, CT 06488.

Lolleez Mixed Berry - Organic 3515-4

Drug Facts

Active ingredient (in each pop)

Pectin 11.5 mg

Purpose

Oral Demulcent

Uses

For temporary relief of minor discomfort of the throat

Warnings

Sore throat warning: If sore throat is severe, persists for more than 2 days, is accompanied or followed by fever, headache, rash, swelling, nausea, or vomiting, consult a doctor promptly. These may be serious.

Stop use and ask a doctor if sore throat does not improve in 7 days.

Keep out of reach of children.

Directions

- Adults and children 3 years of age and older: allow one pop to dissolve slowly in mouth. May be repeated as needed or as directed by a doctor.
- Children under 3 years of age: ask a doctor

Other information

Store at temperatures between 65 and 75 degrees Fahrenheit

Inactive ingredients

citric acid, organic apple juice concentrate, organic blackberry juice concentrate, organic blueberry juice concentrate, organic cane sugar, organic cherry juice concentrate, organic cranberry juice concentrate, organic elderberry juice concentrate, organic flavor, organic honey, organic pear juice concentrate, organic raspberry juice concentrate, organic raspberry powder, organic rice syrup

Questions?

Visit our website at www.momeezchoice.com

Lolleez Mixed Berry - Organic 3515-5

Drug Facts

Active Ingredient (in each pop)

Pectin 11.5 mg

Purpose

Oral Demulcent

Uses

for temporary relief of minor discomfort of the throat

Warnings

Sore throat warning: If sore throat is severe, persists for more than 2 days, is accompanied or followed by fever, headache, rash, nausea, or vomiting, consult a doctor promptly. If sore mouth symptoms do not improve in 7 days, see your dentist or doctor promptly.

Stop use and ask a doctor if

- sore throat does not improve in 7 days
- irritation, pain, or redness persists or worsens

Keep out of reach of children.

Directions

- Adults and children 3 years of age and older: allow one pop to dissolve slowly in mouth
- May be repeated as needed or as directed by a doctor
- Children under 3 years of age: ask a doctor

Other information

store in a dry place between 65°-75°F with package sealed

Inactive ingredients

citric acid, organic apple juice concentrate, organic blackberry juice concentrate, organic blueberry juice concentrate, organic cane sugar, organic cherry juice concentrate, organic cranberry juice concentrate, organic elderberry juice concentrate, organic flavor, organic honey, organic pear juice concentrate, organic raspberry juice concentrate, organic raspberry powder, organic rice syrup

Questions?

Visit our website at www.theEEZco.com, or write us at 450 Heritage Rd., Southbury, CT 06488.

Lolleez Birthday Cake - Organic 4415-1

Drug Facts

Active Ingredient (in each pop)

Pectin 11.5 mg

Purpose

Oral Demulcent

Uses

for temporary relief of minor discomfort of the throat

Warnings

Sore throat warning: If sore throat is severe, persists for more than 2 days, is accompanied or followed by fever, headache, rash, swelling, nausea or vomiting, consult a doctor promptly. These may be serious.

Stop use and ask a doctor if

- sore throat does not improve in 7 days
- irritation, pain, or redness persists or worsens

Keep out of reach of children.

Directions

- Adults and children 3 years of age and older: allow one pop to dissolve slowly in mouth.
- May be repeated as needed or as directed by a doctor
- Children under 3 years of age: ask a doctor

Other information

store at temperatures between 65 and 75 degrees Fahrenheit

Inactive ingredients

organic cane sugar, organic flavors, organic honey, organic rice syrup, organic sprinkles (organic sugar, organic corn starch, organic flavor, natural colors).

Questions?

Visit our website at www.momeezchoice.com

Lolleez Birthday Cake - Conventional 4615-1

Drug Facts

Active Ingredient (in each pop)

Pectin 11.5 mg

Purpose

Oral Demulcent

Uses

for temporary relief of minor discomfort of the throat

Warnings

Sore throat warning: If sore throat is severe, persists for more than 2 days, is accompanied or followed by fever, headache, rash, nausea, or vomitting, consult a doctor promptly. If sore mouth symptoms do not improve in 7 days, see your dentist or doctor promptly.

Stop use and ask a doctor if

- sore throat does not improve in 7 days
- irritation, pain, or redness persists or worsens

Keep out of reach of children.

Directions

- Adults and children 3 years of age and older: allow one pop to dissolve slowly in mouth
- May be repeated as needed or as directed by a doctor
- Children under 3 years of age: ask a doctor

Other information

store in a dry place between 65°-75°F with pouch sealed

Inactive ingredients

carnauba wax, corn starch (NGMO), organic cane sugar, organic flavors, organic honey, organic rice syrup, spirulina extract [color], turmeric [color], and vegetable juice concentrate (extracts of beet, beta-carotene (from carrots), paprika, radish) [color]

Questions?

Visit our website at www.theEEZco.com, or write us at 450 Heritage Rd., Southbury, CT 06488.

Lolleez Birthday Cake - Conventional 4615-2

Drug Facts

Active Ingredient (in each pop)

Pectin 11.5 mg

Purpose

Oral Demulcent

Uses

for temporary relief of minor discomfort of the throat

Warnings

Sore throat warning: If sore throat is severe, persists for more than 2 days, is accompanied or followed by fever, headache, rash, nausea, or vomiting, consult a doctor promptly. If sore mouth symptoms do not improve in 7 days, see your dentist or doctor promptly.

Stop use and ask a doctor if

- sore throat does not improve in 7 days
- irritation, pain, or redness persists or worsens

Keep out of reach of children.

Directions

- Adults and children 3 years of age and older: allow one pop to dissolve slowly in mouth
- May be repeated as needed or as directed by a doctor
- Children under 3 years of age: ask a doctor

Other information

store in a dry place between 65°-75°F with pouch sealed

Inactive ingredients

carnauba wax, corn starch (NGMO), organic cane sugar, organic flavors, organic honey, organic rice syrup, spirulina extract [color], turmeric [color], and vegetable juice concentrate (extracts of beet, beta-carotene (from carrots), paprika, radish) [color]

Questions?

Visit our website at www.theEEZco.com, or write us at 450 Heritage Rd., Southbury, CT 06488.

Lolleez Birthday Cake - Conventional 4615-3

Drug Facts

Active Ingredient (in each pop)

Pectin 11.5 mg

Purpose

Oral Demulcent

Uses

for temporary relief of minor discomfort of the throat

Warnings

Sore throat warning: If sore throat is severe, persists for more than 2 days, is accompanied or followed by fever, headache, rash, nausea, or vomiting, consult a doctor promptly. If sore mouth symptoms do not improve in 7 days, see your dentist or doctor promptly.

Stop use and ask a doctor if

- sore throat does not improve in 7 days
- irritation, pain, or redness persists or worsens

Keep out of reach of children.

Directions

- Adults and children 3 years of age and older: allow one pop to dissolve slowly in mouth
- May be repeated as needed or as directed by a doctor
- Children under 3 years of age: ask a doctor

Other information

store in a dry place between 65°-75°F with pouch sealed

Inactive ingredients

carnauba wax, corn starch (NGMO), organic cane sugar, organic flavors, organic honey, organic rice syrup, spirulina extract [color], turmeric [color], and vegetable juice concentrate (extracts of beet, beta-carotene (from carrots), paprika, radish) [color]

Questions?

Visit our website at www.theEEZco.com, or write us at 450 Heritage Rd., Southbury, CT 06488.

Lolleez Birthday Cake - Conventional 4615-4

Drug Facts

Active Ingredient (in each pop)

Pectin 11.5 mg

Purpose

Oral Demulcent

Uses

for temporary relief of minor discomfort of the throat

Warnings

Sore throat warning: If sore throat is severe, persists for more than 2 days, is accompanied or followed by fever, headache, rash, nausea, or vomiting, consult a doctor promptly. If sore mouth symptoms do not improve in 7 days, see your dentist or doctor promptly.

Stop use and ask a doctor if

- sore throat does not improve in 7 days
- irritation, pain, or redness persists or worsens

Keep out of reach of children.

Directions

- Adults and children 3 years of age and older: allow one pop to dissolve slowly in mouth
- May be repeated as needed or as directed by a doctor
- Children under 3 years of age: ask a doctor

Other information

store in a dry place between 65°-75°F with package sealed

Inactive ingredients

carnauba wax, corn starch (NGMO), organic cane sugar, organic flavors, organic honey, organic rice syrup, spirulina extract [color], turmeric [color], and vegetable juice concentrate (extracts of beet, beta-carotene (from carrots), paprika, radish) [color]

Questions?

Visit our website at www.theEEZco.com, or write us at 450 Heritage Rd., Southbury, CT 06488.

Tumeez Variety Pack - Organic 6010-1

Drug Facts

Active ingredient (in each pop)

Calcium carbonate 200 mg (calcium 80 mg)

Purpose

Antacid

Uses

Relieves: heartburn, sour stomach, acid indigestion

Warnings

Ask a doctor or pharmacist before use if the child is: presently taking a prescription drug. Antacids may interact with certain prescription drugs.

Stop use and ask a doctor if

- symptoms last more than 2 weeks

Keep this and all drugs out of the reach of children.

Directions

- Find the right dose on the chart below based on weight (preferred), otherwise use age.
- Repeat dose as needed.
- Do not take more than 6 pops (ages 3 to 5) or 12 pops (ages 6 to 12) in a 24-hour period, or use the maximum dosage for more than two weeks, except under the advice and supervision of a doctor.

Dosing Chart
Weight (lbs.) | Age | Dose
24 to 47 | 3 to 5 years | 200mg orally up to 6 pops per day
48 to 95 | 6 to 12 years | 200mg orally up to 12 pops per day

Other information

each pop contains 80mg calcium; store at room temperature and avoid excessive humidity.

Inactive ingredients

Apple: organic apple flavor, organic apple juice concentrate, organic apple powder, organic cane sugar, organic honey, organic rice syrup. Grape: organic cane sugar, organic grape flavor, organic grape juice concentrate, organic honey, organic rice syrup.

Questions?

Visit our website at www.momeezchoice.com

Tumeez Variety Pack - Organic 6010-2

Drug Facts

Active ingredient (in each pop)

Calcium carbonate 200 mg (calcium 80 mg)

Purpose

Antacid

Uses

Relieves: heartburn, sour stomach, acid indigestion

Warnings

Ask a doctor or pharmacist before use if the child is: presently taking a prescription drug. Antacids may interact with certain prescription drugs

Stop use and ask a doctor if

- symptoms last more than 2 weeks

Keep this and all drugs out of the reach of children.

Directions

- Find the right dose on the chart based on weight (preferred), otherwise use age.
- Repeat dose as needed.
- Do not take more than 6 pops (ages 3 to 5) or 12 pops (ages 6 to 12) in a 24-hour period, or use the maximum dosage for more than two weeks, except under the advice and supervision of a doctor.

Dosage Chart
Weight (lbs.) | Age | Dose
24 to 47 | 3 to 5 years | 200mg orally up to 6 pops per day
48 to 95 | 6 to 12 years | 200mg orally up to 12 pops per day

Other information

each pop contains 80mg calcium • store at room temperature and avoid excessive humidity.

Inactive ingredients

Apple: organic apple flavor, organic apple juice concentrate, organic apple powder, organic cane sugar, organic honey, organic rice syrup. Grape: organic cane sugar, organic grape flavor, organic grape juice concentrate, organic honey, organic rice syrup.

Questions?

Visit our website at www.momeezchoice.com

Tumeez Variety Pack - Organic 6010-3

Drug Facts

Active Ingredient (in each pop)

Calcium carbonate 200mg (calcium 80mg)

Purpose

Antacid

Uses

Relieves: • heartburn • sour stomach • acid indigestion

Warnings

- Ask a doctor or pharmacist before use if the child is: presently taking a prescription drug. Antacids may interact with certain prescription drugs.
- Do not take more than 6 pops (ages 3 to 5) to 12 pops (ages 6 to 12) in a 24-hour period, or use the maximum dosage for more than two weeks, except under the advice and supervision of a doctor

Stop use and ask a doctor if

- symptoms last more than 2 weeks

Keep out of reach of children.

Directions

- Find the right dose on the chart below based on weight (preferred), otherwise use age
- Repeat dose as needed

Dosing Chart
Weight (lbs.) | Age | Dose
24 to 47 | 3 to 5 years | 200 mg orally up to 6 pops per day
48 to 95 | 6 to 12 years | 200 mg orally up to 12 pops per day

Inactive ingredients

Apple: organic apple flavor, organic apple juice concentrate, organic apple powder, organic cane sugar, organic honey, organic rice syrup. Grape: organic cane sugar, organic grape flavor, organic grape juice concentrate, organic honey, organic rice syrup

Other information

• each pop contains 80 mg calcium • store in a dry place between 65°-75°F with pouch sealed

Questions?

Visit our website at www.theEEZco.com, or write us at 450 Heritage Rd., Southbury, CT 06488.

Tumeez Variety Pack - Organic 6010-4

Drug Facts

Active Ingredient (in each pop)

Calcium carbonate 200mg (calcium 80mg)

Purpose

Antacid

Uses

Relieves:

- heartburn
- sour stomach
- acid indigestion

Warnings

- Ask a doctor or pharmacist before use if the child is: presently taking a prescription drug. Antacids may interact with certain prescription drugs.
- Do not take more than 6 pops (ages 3 to 5) to 12 pops (ages 6 to 12) in a 24-hour period, or use the maximum dosage for more than two weeks, except under the advice and supervision of a doctor

Stop use and ask a doctor if

- symptoms last more than 2 weeks

Keep out of reach of children.

Directions

- Find the right dose on the chart below based on weight (preferred), otherwise use age
- Repeat dose as needed

Dosing Chart
Weight (lbs.) | Age | Dose
24 to 47 | 3 to 5 years | 200 mg orally up to 6 pops per day
48 to 95 | 6 to 12 years | 200 mg orally up to 12 pops per day

Other information

- each pop contains 80 mg calcium
- store in a dry place between 65°-75°F with pouch sealed

Inactive ingredients

Apple: organic apple flavor, organic apple juice concentrate, organic apple powder, organic cane sugar, organic honey, organic rice syrup. Grape: organic cane sugar, organic grape flavor, organic grape juice concentrate, organic honey, organic rice syrup

Questions?

Visit our website at www.theEEZco.com, or write us at 450 Heritage Rd., Southbury, CT 06488.

Sootheez Birthday Cake - Organic 4114-1

Drug Facts

Active Ingredient (in each drop)

Pectin 11.5 mg

Purpose

Oral Demulcent

Uses

for temporary relief of minor discomfort of the throat

Warnings

Sore throat warning: if sore throat is severe, persists for more than 2 days, is accompanied or followed by fever, headache, rash, nausea, or vomiting, consult a doctor promptly. If sore mouth symptoms do not improve in 7 days, see your dentist or doctor promptly.

Stop use and ask a doctor if

- sore throat does not improve in 7 days
- irritation, pain, or redness persists or worsens

Keep out of reach of children.

Directions

- Adults and children 10 years of age and older: allow one drop to dissolve slowly in mouth
- May be repeated as needed or as directed by a doctor
- Children under 10 years of age: ask a doctor

Other information

store in a dry place between 65°-75°F with tin sealed

Inactive ingredients

organic cane sugar, organic honey, organic natural flavors, organic rice syrup

Questions?

Visit our website at www.theEEZco.com, or write us at 450 Heritage Rd., Southbury, CT 06488

Sootheez Birthday Cake - Organic 4114-2

Drug Facts

Active Ingredient (in each drop)

Pectin 11.5 mg

Purpose

Oral Demulcent

Uses

for temporary relief of minor discomfort of the throat

Warnings

Sore throat warning: If sore throat is severe, persists for more than 2 days, is accompanied or followed by fever, headache, rash, nausea, or vomiting, consult a doctor promptly. If sore mouth symptoms do not improve in 7 days, see your dentist or doctor promptly.

Stop use and ask a doctor if

- sore throat does not improve in 7 days
- irritation, pain, or redness persists or worsens

Keep out of reach of children.

Directions

- Adults and children 10 years of age and older: allow one drop to dissolve slowly in mouth
- May be repeated as needed or as directed by a doctor
- Children under 10 years of age: ask a doctor

Other information

store in a dry place between 65°-75°F with tin sealed

Inactive ingredients

organic cane sugar, organic honey, organic natural flavors, organic rice syrup

Questions?

Visit our website at www.theEEZco.com, or write us at 450 Heritage Rd., Southbury, CT 06488.

Sootheez Berry Lemonade - Organic 4014-1

Drug Facts

Active Ingredient (in each drop)

Pectin 11.5 mg

Purpose

Oral Demulcent

Uses

for temporary relief of minor discomfort of the throat

Warnings

Sore throat warning: if sore throat is severe, persists for more than 2 days, is accompanied or followed by fever, headache, rash, nausea, or vomiting, consult a doctor promptly. If sore mouth symptoms do not improve in 7 days, see your dentist or doctor promptly.

Stop use and ask a doctor if

- sore throat does not improve in 7 days
- irritation, pain, or redness persists or worsens

Keep out of reach of children.

Directions

- Adults and children 10 years of age and older: allow one drop to dissolve slowly in mouth
- May be repeated as needed or as directed by a doctor
- Children under 10 years of age: ask a doctor

Other information

store in a dry place between 65°-75°F with tin sealed

Inactive ingredients

citric acid, organic cane sugar, organic honey, organic lemon flavor, organic lemon juice concentrate, organic lemon powder, organic raspberry flavor, organic raspberry juice concentrate, organic raspberry powder, organic rice syrup, organic strawberry juice concentrate, organic vegetable juice concentrate (carrot, radish)

Questions?

Visit our website at www.theEEZco.com, or write us at 450 Heritage Rd., Southbury, CT 06488

Sootheez Berry Lemonade - Organic 4014-2

Drug Facts

Active Ingredient (in each drop)

Pectin 11.5 mg

Purpose

Oral Demulcent

Uses

for temporary relief of minor discomfort of the throat

Warnings

Sore throat warning: If sore throat is severe, persists for more than 2 days, is accompanied or followed by fever, headache, rash, nausea, or vomiting, consult a doctor promptly. If sore mouth symptoms do not improve in 7 days, see your dentist or doctor promptly.

Stop use and ask a doctor if

- sore throat does not improve in 7 days
- irritation, pain, or redness persists or worsens

Keep out of reach of children.

Directions

- Adults and children 10 years of age and older: allow one drop to dissolve slowly in mouth
- May be repeated as needed or as directed by a doctor
- Children under 10 years of age: ask a doctor

Other information

store in a dry place between 65°-75°F with tin sealed

Inactive ingredients

citric acid, organic cane sugar, organic honey, organic lemon flavor, organic lemon juice concentrate, organic lemon powder, organic raspberry flavor, organic raspberry juice concentrate, organic raspberry powder, organic rice syrup, organic strawberry juice concentrate, organic vegetable juice concentrate (carrot, radish)

Questions?

Visit our website at www.theEEZco.com, or write us at 450 Heritage Rd., Southbury, CT 06488.

Sootheez Watermelon Mint - Organic 4314-1

Drug Facts

Active Ingredient (in each drop)

Pectin 11.5 mg

Purpose

Oral Demulcent

Uses

for temporary relief of minor discomfort of the throat

Warnings

Sore throat warning: if sore throat is severe, persists for more than 2 days, is accompanied or followed by fever, headache, rash, nausea, or vomiting, consult a doctor promptly. If sore mouth symptoms do not improve in 7 days, see your dentist or doctor promptly.

Stop use and ask a doctor if

- sore throat does not improve in 7 days
- irritation, pain, or redness persists or worsens

Keep out of reach of children.

Directions

- Adults and children 10 years of age and older: allow one drop to dissolve slowly in mouth
- May be repeated as needed or as directed by a doctor
- Children under 10 years of age: ask a doctor

Other information

store in a dry place between 65°-75°F with tin sealed

Inactive ingredients

citric acid, organic apple juice concentrate, organic cane sugar, organic grape juice concentrate, organic honey, organic mint flavor, organic raspberry powder, organic rice syrup, organic strawberry powder, organic vegetable juice concentrate (carrot, radish), organic watermelon flavor, organic wildberry juice concentrate

Questions?

Visit our website at www.theEEZco.com, or write us at 450 Heritage Rd., Southbury, CT 06488

Sootheez Watermelon Mint - Organic 4314-2

Drug Facts

Active Ingredient (in each drop)

Pectin 11.5 mg

Purpose

Oral Demulcent

Uses

for temporary relief of minor discomfort of the throat

Warnings

Sore throat warning: If sore throat is severe, persists for more than 2 days, is accompanied or followed by fever, headache, rash, nausea, or vomiting, consult a doctor promptly. If sore mouth symptoms do not improve in 7 days, see your dentist or doctor promptly.

Stop use and ask a doctor if

- sore throat does not improve in 7 days
- irritation, pain, or redness persists or worsens

Keep out of reach of children.

Directions

- Adults and children 10 years of age and older: allow one drop to dissolve slowly in mouth
- May be repeated as needed or as directed by a doctor
- Children under 10 years of age: ask a doctor

Other information

store in a dry place between 65°-75°F with tin sealed

Inactive ingredients

citric acid, organic apple juice concentrate, organic cane sugar, organic grape juice concentrate, organic honey, organic mint flavor, organic raspberry powder, organic rice syrup, organic strawberry powder, organic vegetable juice concentrate (carrot, radish), organic watermelon flavor, organic wildberry juice concentrate

Questions?

Visit our website at www.theEEZco.com, or write us at 450 Heritage Rd., Southbury, CT 06488.

Sootheez Strawberry Lemonade - Organic 4214-1

Drug Facts

Active Ingredient (in each drop)

Pectin 11.5 mg

Purpose

Oral Demulcent

Uses

for temporary relief of minor discomfort of the throat

Warnings

Sore throat warning: if sore throat is severe, persists for more than 2 days, is accompanied or followed by fever, headache, rash, nausea, or vomiting, consult a doctor promptly. If sore mouth symptoms do not improve in 7 days, see your dentist or doctor promptly.

Stop use and ask a doctor if

- sore throat does not improve in 7 days
- irritation, pain, or redness persists or worsens

Keep out of reach of children.

Directions

- Adults and children 10 years of age and older: allow one drop to dissolve slowly in mouth
- May be repeated as needed or as directed by a doctor
- Children under 10 years of age: ask a doctor

Other information

store in a dry place between 65°-75°F with tin sealed

Inactive ingredients

citric acid, organic apple juice concentrate, organic cane sugar, organic honey, organic lemon flavor, organic lemon juice concentrate, organic lemon powder, organic raspberry powder, organic rice syrup, organic strawberry flavor, organic strawberry juice concentrate, organic strawberry powder, organic vegetable juice concentrate (carrot, radish)

Questions?

Visit our website at www.theEEZco.com, or write us at 450 Heritage Rd., Southbury, CT 06488

RECENT MAJOR CHANGES

None